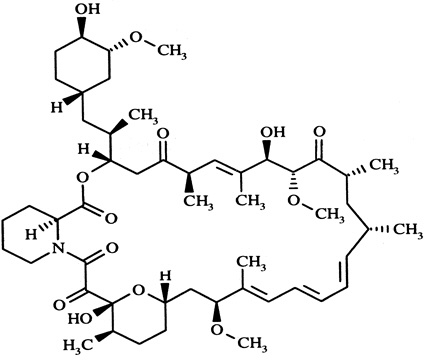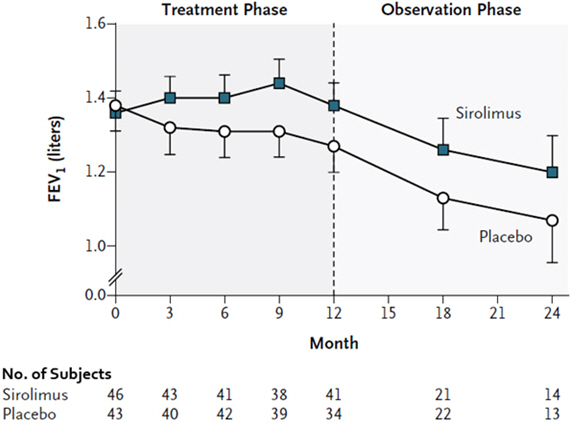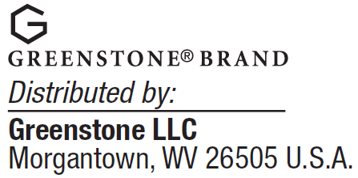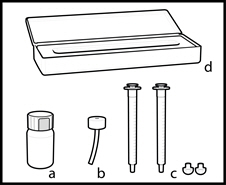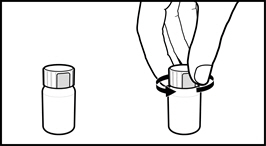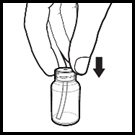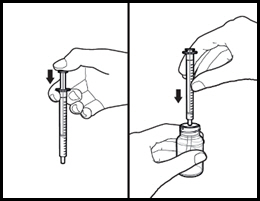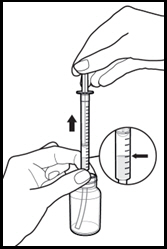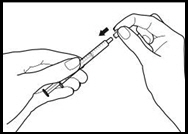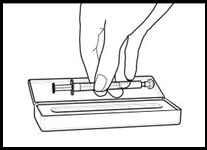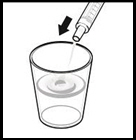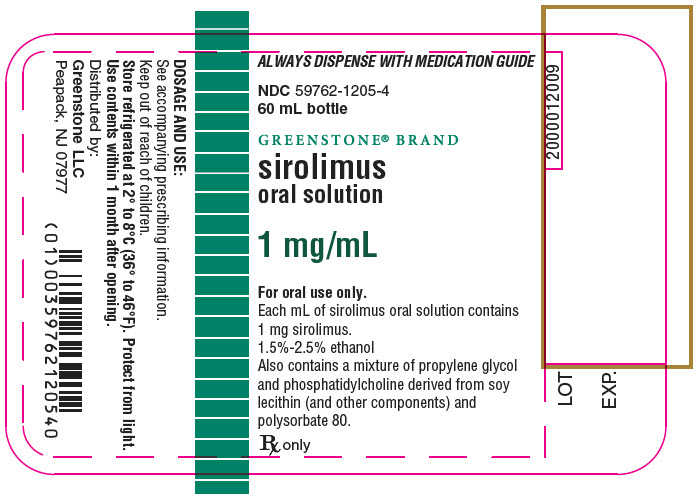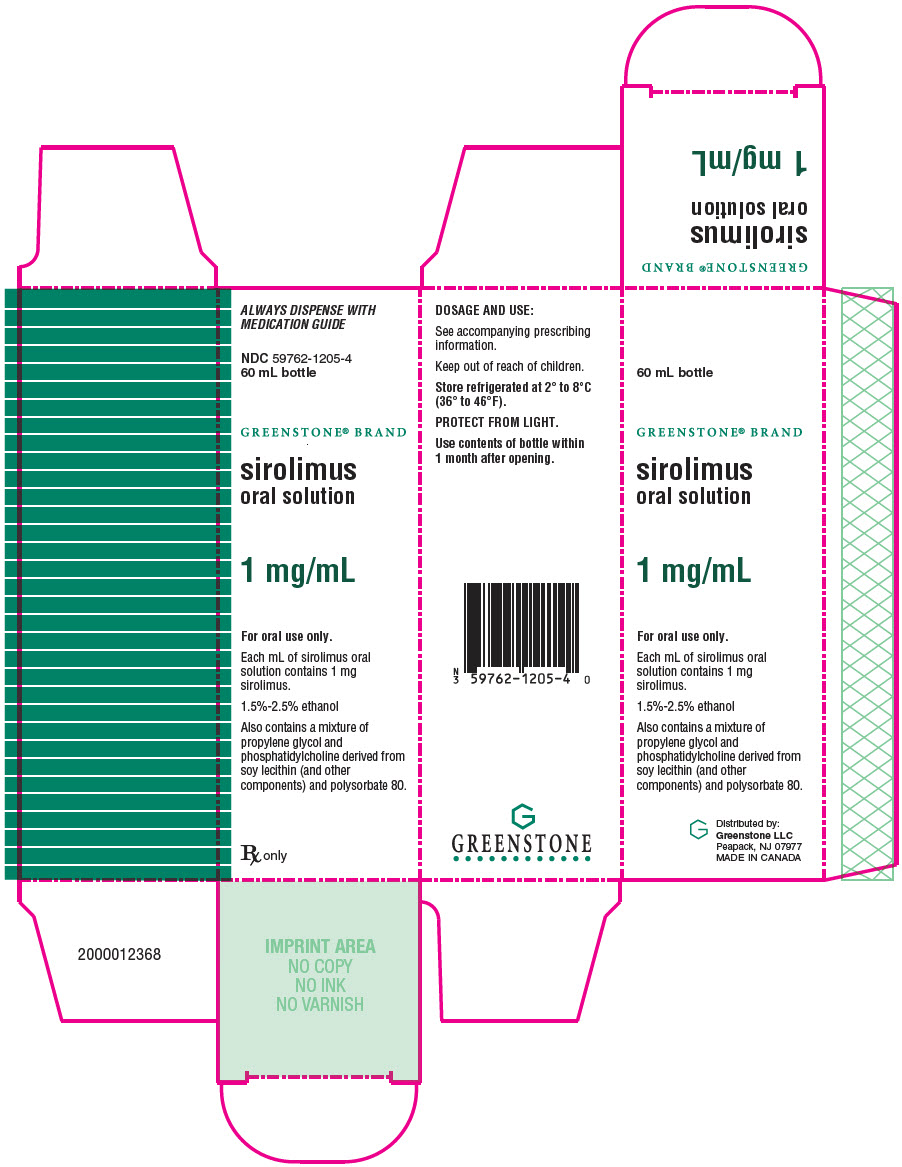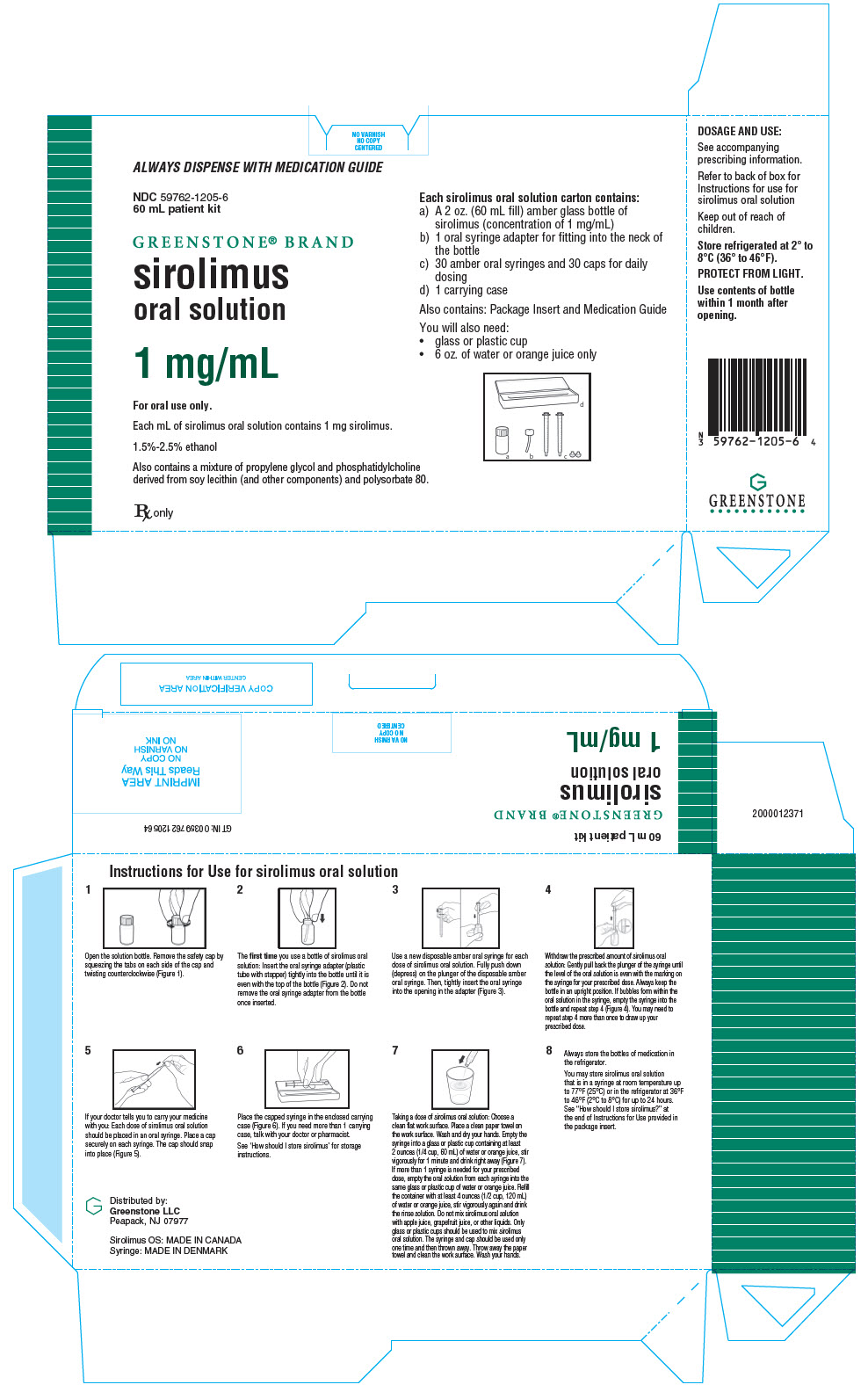 DRUG LABEL: Sirolimus
NDC: 59762-1205 | Form: SOLUTION
Manufacturer: Mylan Pharmaceuticals Inc.
Category: prescription | Type: HUMAN PRESCRIPTION DRUG LABEL
Date: 20250527

ACTIVE INGREDIENTS: SIROLIMUS 1 mg/1 mL
INACTIVE INGREDIENTS: PROPYLENE GLYCOL; POLYSORBATE 80; SOYBEAN PHOSPHATIDYLCHOLINE; ASCORBYL PALMITATE; GLYCERYL MONO- AND DIPALMITOSTEARATE; ALCOHOL; SOY ACID

HIGHLIGHTS OF PRESCRIBING INFORMATION

These highlights do not include all the information needed to use SIROLIMUS safely and effectively. See full prescribing information for SIROLIMUS.
SIROLIMUS oral solution
Initial U.S. Approval: 1999

WARNING: IMMUNOSUPPRESSION, USE IS NOT RECOMMENDED IN LIVER OR LUNG TRANSPLANT PATIENTS

See full prescribing information for complete boxed warning.

- Increased susceptibility to infection and the possible development of lymphoma and other malignancies may result from immunosuppression (5.1). Only physicians experienced in immunosuppressive therapy and management of renal transplant patients should use sirolimus for prophylaxis of organ rejection in patients receiving renal transplants.
- The safety and efficacy of sirolimus as immunosuppressive therapy have not been established in liver or lung transplant patients, and therefore, such use is not recommended (5.2, 5.3).
  - Liver Transplantation – Excess mortality, graft loss, and hepatic artery thrombosis (5.2).
  - Lung Transplantation – Bronchial anastomotic dehiscence (5.3).

1 INDICATIONS AND USAGE

Sirolimus is an mTOR inhibitor immunosuppressant indicated for the prophylaxis of organ rejection in patients aged ≥13 years receiving renal transplants:

- Patients at low- to moderate-immunologic risk: Use initially with cyclosporine (CsA) and corticosteroids. CsA withdrawal is recommended 2–4 months after transplantation (1.1).
- Patients at high-immunologic risk: Use in combination with CsA and corticosteroids for the first 12 months following transplantation (1.1). Safety and efficacy of CsA withdrawal has not been established in high risk patients (1.1, 1.2, 14.3).

Sirolimus is an mTOR inhibitor indicated for the treatment of patients with lymphangioleiomyomatosis (1.3).

2 DOSAGE AND ADMINISTRATION

Renal Transplant Patients:

- Administer once daily by mouth, consistently with or without food (2).
- Administer the initial dose as soon as possible after transplantation and 4 hours after CsA (2.1, 7.1).
- Adjust the sirolimus maintenance dose to achieve sirolimus trough concentrations within the target-range (2.5).
- Hepatic impairment: Reduce maintenance dose in patients with hepatic impairment (2.7, 8.6, 12.3).

In renal transplant patients at low- to moderate-immunologic risk:

- Sirolimus and CsA Combination Therapy: One loading dose of 6 mg on day 1, followed by daily maintenance doses of 2 mg (2.2).
- Sirolimus Following CsA Withdrawal: 2–4 months post-transplantation, withdraw CsA over 4–8 weeks (2.2).

In renal transplant patients at high-immunologic risk:

- Sirolimus and CsA Combination Therapy (for the first 12 months post-transplantation): One loading dose of up to 15 mg on day 1, followed by daily maintenance doses of 5 mg (2.3).

Lymphangioleiomyomatosis Patients:

- Administer once daily by mouth, consistently with or without food (2).
- Recommended initial sirolimus dose is 2 mg/day (2.4).
- Adjust the sirolimus dose to achieve sirolimus trough concentrations between 5–15 ng/mL (2.4).
- Hepatic impairment: Reduce maintenance dose in patients with hepatic impairment (2.7, 8.6, 12.3).

Therapeutic drug monitoring is recommended for all patients (2.5, 5.17).

3 DOSAGE FORMS AND STRENGTHS

- Oral Solution: 60 mg per 60 mL in amber glass bottle (3.1)

4 CONTRAINDICATIONS

Hypersensitivity to sirolimus (4)

5 WARNINGS AND PRECAUTIONS

- Hypersensitivity Reactions (5.4)
- Angioedema (5.5)
- Fluid Accumulation and Impairment of Wound Healing (5.6)
- Hyperlipidemia (5.7)
- Decline in Renal Function (5.8)
- Proteinuria (5.9)
- Latent Viral Infections (5.10)
- Interstitial Lung Disease/Non-Infectious Pneumonitis (5.11)
- De Novo Use Without Cyclosporine (5.12)
- Increased Risk of Calcineurin Inhibitor-Induced Hemolytic Uremic Syndrome/ Thrombotic Thrombocytopenic Purpura/ Thrombotic Microangiopathy (5.13).
- Embryo-Fetal Toxicity: Can cause fetal harm. Use of highly effective contraception is recommended for females of reproductive potential during treatment and for 12 weeks after final dose of sirolimus (5.15, 8.1).
- Male Infertility: Azoospermia or oligospermia may occur (5.16, 13.1)
- Immunizations: Avoid live vaccines (5.19)

6 ADVERSE REACTIONS

Prophylaxis of organ rejection in patients receiving renal transplants: Most common adverse reactions (incidence ≥30%) are peripheral edema, hypertriglyceridemia, hypertension, hypercholesterolemia, creatinine increased, abdominal pain, diarrhea, headache, fever, urinary tract infection, anemia, nausea, arthralgia, pain, and thrombocytopenia (6).

Lymphangioleiomyomatosis: Most common adverse reactions (incidence ≥20%) are stomatitis, diarrhea, abdominal pain, nausea, nasopharyngitis, acne, chest pain, peripheral edema, upper respiratory tract infection, headache, dizziness, myalgia, and hypercholesterolemia (6.6).

To report SUSPECTED ADVERSE REACTIONS, contact Greenstone LLC Professional Information Services at 1-877-446-3679 or FDA at 1-800-FDA-1088 or www.fda.gov/medwatch.

7 DRUG INTERACTIONS

- Avoid concomitant use with strong CYP3A4/P-gp inducers or strong CYP3A4/P-gp inhibitors that decrease or increase sirolimus concentrations (7.4, 12.3).
- Therapeutic drug monitoring and dose reduction for sirolimus should be considered when sirolimus is co-administered with cannabidiol (5.21, 7.5).
- See full prescribing information for complete list of clinically significant drug interactions (12.3).

8 USE IN SPECIFIC POPULATIONS

- Pregnancy: Based on animal data can cause fetal harm (5.15, 8.1).
- Lactation: Potential for serious adverse effects in breastfed infants based on mechanism of action (8.2).
- Females and Males of Reproductive Potential: May impair fertility (8.1, 8.3, 13.1).

FULL PRESCRIBING INFORMATION

WARNING: IMMUNOSUPPRESSION, USE IS NOT RECOMMENDED IN LIVER OR LUNG TRANSPLANT PATIENTS

- Increased susceptibility to infection and the possible development of lymphoma and other malignancies may result from immunosuppression

Increased susceptibility to infection and the possible development of lymphoma may result from immunosuppression. Only physicians experienced in immunosuppressive therapy and management of renal transplant patients should use sirolimus for prophylaxis of organ rejection in patients receiving renal transplants. Patients receiving the drug should be managed in facilities equipped and staffed with adequate laboratory and supportive medical resources. The physician responsible for maintenance therapy should have complete information requisite for the follow-up of the patient [see Warnings and Precautions (5.1)].

- The safety and efficacy of sirolimus as immunosuppressive therapy have not been established in liver or lung transplant patients, and therefore, such use is not recommended [see Warnings and Precautions (5.2, 5.3)].
- Liver Transplantation – Excess Mortality, Graft Loss, and Hepatic Artery Thrombosis (HAT)

The use of sirolimus in combination with tacrolimus was associated with excess mortality and graft loss in a study in de novo liver transplant patients. Many of these patients had evidence of infection at or near the time of death.

In this and another study in de novo liver transplant patients, the use of sirolimus in combination with cyclosporine or tacrolimus was associated with an increase in HAT; most cases of HAT occurred within 30 days post-transplantation and most led to graft loss or death [see Warnings and Precautions (5.2)].

- Lung Transplantation – Bronchial Anastomotic Dehiscence

Cases of bronchial anastomotic dehiscence, most fatal, have been reported in de novo lung transplant patients when sirolimus has been used as part of an immunosuppressive regimen [see Warnings and Precautions (5.3)].

1 INDICATIONS AND USAGE

1.1 Prophylaxis of Organ Rejection in Renal Transplantation

Sirolimus is indicated for the prophylaxis of organ rejection in patients aged 13 years or older receiving renal transplants.

In patients at low- to moderate-immunologic risk, it is recommended that sirolimus be used initially in a regimen with cyclosporine and corticosteroids; cyclosporine should be withdrawn 2 to 4 months after transplantation [see Dosage and Administration (2.2)].

In patients at high-immunologic risk (defined as Black recipients and/or repeat renal transplant recipients who lost a previous allograft for immunologic reason and/or patients with high panel-reactive antibodies [PRA; peak PRA level >80%]), it is recommended that sirolimus be used in combination with cyclosporine and corticosteroids for the first year following transplantation [see Dosage and Administration (2.3), Clinical Studies (14.3)].

1.2 Limitations of Use in Renal Transplantation

Cyclosporine withdrawal has not been studied in patients with Banff Grade 3 acute rejection or vascular rejection prior to cyclosporine withdrawal, those who are dialysis-dependent, those with serum creatinine >4.5 mg/dL, Black patients, patients of multi-organ transplants, secondary transplants, or those with high levels of panel-reactive antibodies [see Clinical Studies (14.2)].

In patients at high-immunologic risk, the safety and efficacy of sirolimus used in combination with cyclosporine and corticosteroids has not been studied beyond one year; therefore after the first 12 months following transplantation, any adjustments to the immunosuppressive regimen should be considered on the basis of the clinical status of the patient [see Clinical Studies (14.3)].

In pediatric patients, the safety and efficacy of sirolimus have not been established in patients <13 years old, or in pediatric (<18 years) renal transplant patients considered at high-immunologic risk [see Adverse Reactions (6.5), Clinical Studies (14.6)].

The safety and efficacy of de novo use of sirolimus without cyclosporine have not been established in renal transplant patients [see Warnings and Precautions (5.12)].

The safety and efficacy of conversion from calcineurin inhibitors to sirolimus in maintenance renal transplant patients have not been established [see Clinical Studies (14.4)].

1.3 Treatment of Patients with Lymphangioleiomyomatosis

Sirolimus is indicated for the treatment of patients with lymphangioleiomyomatosis (LAM).

2 DOSAGE AND ADMINISTRATION

Sirolimus is to be administered orally once daily, consistently with or without food [see Dosage and Administration (2.5), Clinical Pharmacology (12.3)].

2.1 General Dosing Guidance for Renal Transplant Patients

The initial dose of sirolimus should be administered as soon as possible after transplantation. It is recommended that sirolimus be taken 4 hours after administration of cyclosporine oral solution (MODIFIED) and or/cyclosporine capsules (MODIFIED) [see Drug Interactions (7.2)].

Frequent sirolimus dose adjustments based on non-steady-state sirolimus concentrations can lead to overdosing or underdosing because sirolimus has a long half-life. Once sirolimus maintenance dose is adjusted, patients should continue on the new maintenance dose for at least 7 to 14 days before further dosage adjustment with concentration monitoring. In most patients, dose adjustments can be based on simple proportion: new sirolimus dose = current dose × (target concentration/current concentration). A loading dose should be considered in addition to a new maintenance dose when it is necessary to increase sirolimus trough concentrations: sirolimus loading dose = 3 × (new maintenance dose - current maintenance dose). The maximum sirolimus dose administered on any day should not exceed 40 mg. If an estimated daily dose exceeds 40 mg due to the addition of a loading dose, the loading dose should be administered over 2 days. Sirolimus trough concentrations should be monitored at least 3 to 4 days after a loading dose(s).

Two milligrams (2 mg) of sirolimus oral solution have been demonstrated to be clinically equivalent to 2 mg sirolimus tablets; hence, at this dose these two formulations are interchangeable. However, it is not known if higher doses of sirolimus oral solution are clinically equivalent to higher doses of sirolimus tablets on a mg-to-mg basis [see Clinical Pharmacology (12.3)].

2.2 Renal Transplant Patients at Low- to Moderate-Immunologic Risk

Sirolimus and Cyclosporine Combination Therapy

For de novo renal transplant patients, it is recommended that sirolimus oral solution and tablets be used initially in a regimen with cyclosporine and corticosteroids. A loading dose of sirolimus equivalent to 3 times the maintenance dose should be given, i.e. a daily maintenance dose of 2 mg should be preceded with a loading dose of 6 mg. Therapeutic drug monitoring should be used to maintain sirolimus drug concentrations within the target-range [see Dosage and Administration (2.5)].

Sirolimus Following Cyclosporine Withdrawal

At 2 to 4 months following transplantation, cyclosporine should be progressively discontinued over 4 to 8 weeks, and the sirolimus dose should be adjusted to obtain sirolimus whole blood trough concentrations within the target-range [see Dosage and Administration (2.5)]. Because cyclosporine inhibits the metabolism and transport of sirolimus, sirolimus concentrations may decrease when cyclosporine is discontinued, unless the sirolimus dose is increased [see Clinical Pharmacology (12.3)].

2.3 Renal Transplant Patients at High-Immunologic Risk

In patients with high-immunologic risk, it is recommended that sirolimus be used in combination with cyclosporine and corticosteroids for the first 12 months following transplantation [see Clinical Studies (14.3)]. The safety and efficacy of this combination in high-immunologic risk patients has not been studied beyond the first 12 months. Therefore, after the first 12 months following transplantation, any adjustments to the immunosuppressive regimen should be considered on the basis of the clinical status of the patient.

For patients receiving sirolimus with cyclosporine, sirolimus therapy should be initiated with a loading dose of up to 15 mg on day 1 post-transplantation. Beginning on day 2, an initial maintenance dose of 5 mg/day should be given. A trough level should be obtained between days 5 and 7, and the daily dose of sirolimus should thereafter be adjusted [see Dosage and Administration (2.5)].

The starting dose of cyclosporine should be up to 7 mg/kg/day in divided doses and the dose should subsequently be adjusted to achieve target whole blood trough concentrations [see Dosage and Administration (2.5)]. Prednisone should be administered at a minimum of 5 mg/day.

Antibody induction therapy may be used.

2.4 Dosing in Patients with Lymphangioleiomyomatosis

For patients with lymphangioleiomyomatosis, the initial Sirolimus dose should be 2 mg/day. Sirolimus whole blood trough concentrations should be measured in 10–20 days, with dosage adjustment to maintain concentrations between 5–15 ng/mL [see Dosage and Administration (2.5)].

In most patients, dose adjustments can be based on simple proportion: new Sirolimus dose = current dose × (target concentration/current concentration). Frequent Sirolimus dose adjustments based on non-steady-state sirolimus concentrations can lead to overdosing or under dosing because sirolimus has a long half-life. Once Sirolimus maintenance dose is adjusted, patients should continue on the new maintenance dose for at least 7 to 14 days before further dosage adjustment with concentration monitoring. Once a stable dose is achieved, therapeutic drug monitoring should be performed at least every three months.

2.5 Therapeutic Drug Monitoring

Monitoring of sirolimus trough concentrations is recommended for all patients, especially in those patients likely to have altered drug metabolism, in patients ≥ 13 years who weigh less than 40 kg, in patients with hepatic impairment, when a change in the sirolimus dosage form is made, and during concurrent administration of strong CYP3A4 inducers and inhibitors [see Warnings and Precautions (5.20, 5.21), Drug Interactions (7)].

Therapeutic drug monitoring should not be the sole basis for adjusting sirolimus therapy. Careful attention should be made to clinical signs/symptoms, tissue biopsy findings, and laboratory parameters.

When used in combination with cyclosporine, sirolimus trough concentrations should be maintained within the target-range [see Clinical Studies (14), Clinical Pharmacology (12.3)]. Following cyclosporine withdrawal in transplant patients at low- to moderate-immunologic risk, the target sirolimus trough concentrations should be 16 to 24 ng/mL for the first year following transplantation. Thereafter, the target sirolimus concentrations should be 12 to 20 ng/mL.

The above recommended 24-hour trough concentration ranges for sirolimus are based on chromatographic methods. Currently in clinical practice, sirolimus whole blood concentrations are being measured by both chromatographic and immunoassay methodologies. Because the measured sirolimus whole blood concentrations depend on the type of assay used, the concentrations obtained by these different methodologies are not interchangeable [see Warnings and Precautions (5.17), Clinical Pharmacology (12.3)]. Adjustments to the targeted range should be made according to the assay utilized to determine sirolimus trough concentrations. Since results are assay and laboratory dependent, and the results may change over time, adjustments to the targeted therapeutic range must be made with a detailed knowledge of the site-specific assay used. Therefore, communication should be maintained with the laboratory performing the assay. A discussion of different assay methods is contained in Clinical Therapeutics, Volume 22, Supplement B, April 2000 [see References (15)].

2.6 Patients with Low Body Weight

The initial dosage in patients ≥13 years who weigh less than 40 kg should be adjusted, based on body surface area, to 1 mg/m^2/day. The loading dose should be 3 mg/m^2.

2.7 Patients with Hepatic Impairment

It is recommended that the maintenance dose of sirolimus be reduced by approximately one third in patients with mild or moderate hepatic impairment and by approximately one half in patients with severe hepatic impairment. It is not necessary to modify the sirolimus loading dose [see Use in Specific Populations (8.6), Clinical Pharmacology (12.3)].

2.8 Patients with Renal Impairment

Dosage adjustment is not needed in patients with impaired renal function [see Use in Specific Populations (8.7)].

2.9 Instructions for Dilution and Administration of Sirolimus Oral Solution

The amber oral dose syringe should be used to withdraw the prescribed amount of sirolimus oral solution from the bottle. Empty the correct amount of sirolimus from the syringe into only a glass or plastic container holding at least two (2) ounces (1/4 cup, 60 mL) of water or orange juice. No other liquids, including grapefruit juice, should be used for dilution [see Drug Interactions (7.3), Clinical Pharmacology (12.3)]. Stir vigorously and drink at once. Refill the container with an additional volume [minimum of four (4) ounces (1/2 cup, 120 mL)] of water or orange juice, stir vigorously, and drink at once.

Sirolimus oral solution contains polysorbate 80, which is known to increase the rate of di-(2-ethylhexyl)phthalate (DEHP) extraction from polyvinyl chloride (PVC). This should be considered during the preparation and administration of sirolimus oral solution. It is important that these recommendations be followed closely.

3 DOSAGE FORMS AND STRENGTHS

3.1 Sirolimus Oral Solution

- 60 mg per 60 mL in amber glass bottle.

4 CONTRAINDICATIONS

Sirolimus is contraindicated in patients with a hypersensitivity to sirolimus [see Warnings and Precautions (5.4)].

5 WARNINGS AND PRECAUTIONS

5.1 Increased Susceptibility to Infection and the Possible Development of Lymphoma

Increased susceptibility to infection and the possible development of lymphoma and other malignancies, particularly of the skin, may result from immunosuppression. The rates of lymphoma/lymphoproliferative disease observed in Studies 1 and 2 were 0.7–3.2% (for sirolimus-treated patients) versus 0.6–0.8% (azathioprine and placebo control) [see Adverse Reactions (6.1) and (6.2)]. Oversuppression of the immune system can also increase susceptibility to infection, including opportunistic infections such as tuberculosis, fatal infections, and sepsis. Only physicians experienced in immunosuppressive therapy and management of organ transplant patients should use sirolimus for prophylaxis of organ rejection in patients receiving renal transplants. Patients receiving the drug should be managed in facilities equipped and staffed with adequate laboratory and supportive medical resources. The physician responsible for maintenance therapy should have complete information requisite for the follow-up of the patient.

5.2 Liver Transplantation – Excess Mortality, Graft Loss, and Hepatic Artery Thrombosis

The safety and efficacy of sirolimus as immunosuppressive therapy have not been established in liver transplant patients; therefore, such use is not recommended. The use of sirolimus has been associated with adverse outcomes in patients following liver transplantation, including excess mortality, graft loss and hepatic artery thrombosis (HAT).

In a study in de novo liver transplant patients, the use of sirolimus in combination with tacrolimus was associated with excess mortality and graft loss (22% in combination versus 9% on tacrolimus alone). Many of these patients had evidence of infection at or near the time of death.

In this and another study in de novo liver transplant patients, the use of sirolimus in combination with cyclosporine or tacrolimus was associated with an increase in HAT (7% in combination versus 2% in the control arm); most cases of HAT occurred within 30 days post-transplantation, and most led to graft loss or death.

In a clinical study in stable liver transplant patients 6–144 months post-liver transplantation and receiving a CNI-based regimen, an increased number of deaths was observed in the group converted to a sirolimus-based regimen compared to the group who was continued on a CNI-based regimen, although the difference was not statistically significant (3.8% versus 1.4%) [see Clinical Studies (14.5)].

5.3 Lung Transplantation – Bronchial Anastomotic Dehiscence

Cases of bronchial anastomotic dehiscence, most fatal, have been reported in de novo lung transplant patients when sirolimus has been used as part of an immunosuppressive regimen.

The safety and efficacy of sirolimus as immunosuppressive therapy have not been established in lung transplant patients; therefore, such use is not recommended.

5.4 Hypersensitivity Reactions

Hypersensitivity reactions, including anaphylactic/anaphylactoid reactions, angioedema, exfoliative dermatitis and hypersensitivity vasculitis, have been associated with the administration of sirolimus [see Adverse Reactions (6.7)].

5.5 Angioedema

Sirolimus has been associated with the development of angioedema. The concomitant use of sirolimus with other drugs known to cause angioedema, such as angiotensin-converting enzyme (ACE) inhibitors, may increase the risk of developing angioedema. Elevated sirolimus levels (with/without concomitant ACE inhibitors) may also potentiate angioedema [see Drug Interactions (7.2)]. In some cases, the angioedema has resolved upon discontinuation or dose reduction of sirolimus.

5.6 Fluid Accumulation and Impairment of Wound Healing

There have been reports of impaired or delayed wound healing in patients receiving sirolimus, including lymphocele and wound dehiscence [see Adverse Reactions (6.1)]. Mammalian target of rapamycin (mTOR) inhibitors such as sirolimus have been shown in vitro to inhibit production of certain growth factors that may affect angiogenesis, fibroblast proliferation, and vascular permeability. Lymphocele, a known surgical complication of renal transplantation, occurred significantly more often in a dose-related fashion in patients treated with sirolimus [see Adverse Reactions (6.1)]. Appropriate measures should be considered to minimize such complications. Patients with a body mass index (BMI) greater than 30 kg/m^2 may be at increased risk of abnormal wound healing based on data from the medical literature.

There have also been reports of fluid accumulation, including peripheral edema, lymphedema, pleural effusion, ascites, and pericardial effusions (including hemodynamically significant effusions and tamponade requiring intervention in children and adults), in patients receiving sirolimus.

5.7 Hyperlipidemia

Increased serum cholesterol and triglycerides requiring treatment occurred more frequently in patients treated with sirolimus compared with azathioprine or placebo controls in Studies 1 and 2 [see Adverse Reactions (6.1)]. There were increased incidences of hypercholesterolemia (43–46%) and/or hypertriglyceridemia (45–57%) in patients receiving sirolimus compared with placebo controls (each 23%). The risk/benefit should be carefully considered in patients with established hyperlipidemia before initiating an immunosuppressive regimen including sirolimus.

Any patient who is administered sirolimus should be monitored for hyperlipidemia. If detected, interventions such as diet, exercise, and lipid-lowering agents should be initiated as outlined by the National Cholesterol Education Program guidelines.

In clinical trials of patients receiving sirolimus plus cyclosporine or sirolimus after cyclosporine withdrawal, up to 90% of patients required treatment for hyperlipidemia and hypercholesterolemia with anti-lipid therapy (e.g., statins, fibrates). Despite anti-lipid management, up to 50% of patients had fasting serum cholesterol levels >240 mg/dL and triglycerides above recommended target levels. The concomitant administration of sirolimus and HMG-CoA reductase inhibitors resulted in adverse reactions such as CPK elevations (3%), myalgia (6.7%) and rhabdomyolysis (<1%). In these trials, the number of patients was too small and duration of follow-up too short to evaluate the long-term impact of sirolimus on cardiovascular mortality.

During sirolimus therapy with or without cyclosporine, patients should be monitored for elevated lipids, and patients administered an HMG-CoA reductase inhibitor and/or fibrate should be monitored for the possible development of rhabdomyolysis and other adverse effects, as described in the respective labeling for these agents.

5.8 Decline in Renal Function

Renal function should be closely monitored during the co-administration of sirolimus with cyclosporine, because long-term administration of the combination has been associated with deterioration of renal function. Patients treated with cyclosporine and sirolimus were noted to have higher serum creatinine levels and lower glomerular filtration rates compared with patients treated with cyclosporine and placebo or azathioprine controls (Studies 1 and 2). The rate of decline in renal function in these studies was greater in patients receiving sirolimus and cyclosporine compared with control therapies.

Appropriate adjustment of the immunosuppressive regimen, including discontinuation of sirolimus and/or cyclosporine, should be considered in patients with elevated or increasing serum creatinine levels. In patients at low- to moderate-immunologic risk, continuation of combination therapy with cyclosporine beyond 4 months following transplantation should only be considered when the benefits outweigh the risks of this combination for the individual patients. Caution should be exercised when using agents (e.g., aminoglycosides and amphotericin B) that are known to have a deleterious effect on renal function.

In patients with delayed graft function, sirolimus may delay recovery of renal function.

5.9 Proteinuria

Periodic quantitative monitoring of urinary protein excretion is recommended. In a study evaluating conversion from calcineurin inhibitors (CNI) to sirolimus in maintenance renal transplant patients 6–120 months post-transplant, increased urinary protein excretion was commonly observed from 6 through 24 months after conversion to sirolimus compared with CNI continuation [see Clinical Studies (14.4), Adverse Reactions (6.4)]. Patients with the greatest amount of urinary protein excretion prior to sirolimus conversion were those whose protein excretion increased the most after conversion. New onset nephrosis (nephrotic syndrome) was also reported as a treatment-emergent adverse reaction in 2.2% of the sirolimus conversion group patients in comparison to 0.4% in the CNI continuation group of patients. Nephrotic range proteinuria (defined as urinary protein to creatinine ratio >3.5) was also reported in 9.2% in the sirolimus conversion group of patients in comparison to 3.7% in the CNI continuation group of patients. In some patients, reduction in the degree of urinary protein excretion was observed for individual patients following discontinuation of sirolimus. The safety and efficacy of conversion from calcineurin inhibitors to sirolimus in maintenance renal transplant patients have not been established.

5.10 Latent Viral Infections

Immunosuppressed patients are at increased risk for opportunistic infections, including activation of latent viral infections. These include BK virus-associated nephropathy, which has been observed in renal transplant patients receiving immunosuppressants, including sirolimus. This infection may be associated with serious outcomes, including deteriorating renal function and renal graft loss [see Adverse Reactions (6.7)]. Patient monitoring may help detect patients at risk for BK virus-associated nephropathy. Reduction in immunosuppression should be considered for patients who develop evidence of BK virus-associated nephropathy.

Cases of progressive multifocal leukoencephalopathy (PML), sometimes fatal have been reported in patients treated with immunosuppressants, including sirolimus. PML commonly presents with hemiparesis, apathy, confusion, cognitive deficiencies and ataxia. Risk factors for PML include treatment with immunosuppressant therapies and impairment of immune function. In immunosuppressed patients, physicians should consider PML in the differential diagnosis in patients reporting neurological symptoms and consultation with a neurologist should be considered as clinically indicated. Consideration should be given to reducing the amount of immunosuppression in patients who develop PML. In transplant patients, physicians should also consider the risk that reduced immunosuppression represents to the graft.

5.11 Interstitial Lung Disease/Non-Infectious Pneumonitis

Cases of interstitial lung disease [ILD] (including pneumonitis, bronchiolitis obliterans organizing pneumonia [BOOP], and pulmonary fibrosis), some fatal, with no identified infectious etiology have occurred in patients receiving immunosuppressive regimens including sirolimus. In some cases, the ILD was reported with pulmonary hypertension (including pulmonary arterial hypertension [PAH]) as a secondary event. In some cases, the ILD has resolved upon discontinuation or dose reduction of sirolimus. The risk may be increased as the trough sirolimus concentration increases [see Adverse Reactions (6.7)].

5.12 De Novo Use Without Cyclosporine

The safety and efficacy of de novo use of sirolimus without cyclosporine is not established in renal transplant patients. In a multicenter clinical study, de novo renal transplant patients treated with sirolimus, mycophenolate mofetil (MMF), steroids, and an IL-2 receptor antagonist had significantly higher acute rejection rates and numerically higher death rates compared to patients treated with cyclosporine, MMF, steroids, and IL-2 receptor antagonist. A benefit, in terms of better renal function, was not apparent in the treatment arm with de novo use of sirolimus without cyclosporine. These findings were also observed in a similar treatment group of another clinical trial.

5.13 Increased Risk of Calcineurin Inhibitor-Induced Hemolytic Uremic Syndrome/Thrombotic Thrombocytopenic Purpura/Thrombotic Microangiopathy

The concomitant use of sirolimus with a calcineurin inhibitor may increase the risk of calcineurin inhibitor-induced hemolytic uremic syndrome/thrombotic thrombocytopenic purpura/thrombotic microangiopathy (HUS/TTP/TMA) [see Adverse Reactions (6.7)].

5.14 Antimicrobial Prophylaxis

Cases of Pneumocystis carinii pneumonia have been reported in transplant patients not receiving antimicrobial prophylaxis. Therefore, antimicrobial prophylaxis for Pneumocystis carinii pneumonia should be administered for 1 year following transplantation.

Cytomegalovirus (CMV) prophylaxis is recommended for 3 months after transplantation, particularly for patients at increased risk for CMV disease.

5.15 Embryo-Fetal Toxicity

Based on animal studies and the mechanism of action [see Clinical Pharmacology (12.1)], sirolimus can cause fetal harm when administered to a pregnant woman. In animal studies, sirolimus caused embryo-fetal toxicity when administered during the period of organogenesis at maternal exposures that were equal to or less than human exposures at the recommended lowest starting dose. Advise pregnant women of the potential risk to a fetus. Advise female patients of reproductive potential to avoid becoming pregnant and to use highly effective contraception while using sirolimus and for 12 weeks after ending treatment [see Use in Specific Populations (8.1)].

5.16 Male Infertility

Azoospermia or oligospermia may be observed [see Adverse Reactions (6.7), Nonclinical Toxicology (13.1)]. Sirolimus is an anti-proliferative drug and affects rapidly dividing cells like the germ cells.

5.17 Different Sirolimus Trough Concentration Reported between Chromatographic and Immunoassay Methodologies

Currently in clinical practice, sirolimus whole blood concentrations are being measured by various chromatographic and immunoassay methodologies. Patient sample concentration values from different assays may not be interchangeable [see Dosage and Administration (2.5)].

5.18 Skin Cancer Events

Patients on immunosuppressive therapy are at increased risk for skin cancer. Exposure to sunlight and ultraviolet (UV) light should be limited by wearing protective clothing and using a broad spectrum sunscreen with a high protection factor [see Adverse Reactions (6.1, 6.2, 6.7)].

5.19 Immunizations

The use of live vaccines should be avoided during treatment with sirolimus; live vaccines may include, but are not limited to, the following: measles, mumps, rubella, oral polio, BCG, yellow fever, varicella, and TY21a typhoid. Immunosuppressants may affect response to vaccination. Therefore, during treatment with sirolimus, vaccination may be less effective.

5.20 Interaction with Strong Inhibitors and Inducers of CYP3A4 and/or P-gp

Avoid concomitant use of sirolimus with strong inhibitors of CYP3A4 and/or P-gp (such as ketoconazole, voriconazole, itraconazole, erythromycin, telithromycin, or clarithromycin) or strong inducers of CYP3A4 and/or P-gp (such as rifampin or rifabutin) [see Drug Interactions (7.2)].

5.21 Cannabidiol Drug Interactions

When cannabidiol and sirolimus are co-administered, closely monitor for an increase in sirolimus blood levels and for adverse reactions suggestive of sirolimus toxicity. A dose reduction of sirolimus should be considered as needed when sirolimus is co-administered with cannabidiol [see Dosage and Administration (2.5), Drug Interactions (7.5)].

6 ADVERSE REACTIONS

The following adverse reactions are discussed in greater detail in other sections of the label.

- Increased susceptibility to infection, lymphoma, and malignancy [see Boxed Warning, Warnings and Precautions (5.1)]
- Excess mortality, graft loss, and hepatic artery thrombosis in liver transplant patients [see Boxed Warning, Warnings and Precautions (5.2)]
- Bronchial anastomotic dehiscence in lung transplant patients [see Boxed Warning, Warnings and Precautions (5.3)]
- Hypersensitivity reactions [see Warnings and Precautions (5.4)]
- Exfoliative dermatitis [see Warnings and Precautions (5.4)]
- Angioedema [see Warnings and Precautions (5.5)]
- Fluid accumulation and impairment of wound healing [see Warnings and Precautions (5.6)]
- Hypertriglyceridemia, hypercholesterolemia [see Warnings and Precautions (5.7)]
- Decline in renal function in long-term combination of cyclosporine with sirolimus [see Warnings and Precautions (5.8)]
- Proteinuria [see Warnings and Precautions (5.9)]
- Interstitial lung disease [see Warnings and Precautions (5.11)]
- Increased risk of calcineurin inhibitor-induced HUS/TTP/TMA [see Warnings and Precautions (5.13)]
- Embryo-fetal toxicity [see Warnings and Precautions (5.15)]
- Male infertility [see Warnings and Precautions (5.16)]

The most common (≥30%) adverse reactions observed with sirolimus in clinical studies for organ rejection prophylaxis in recipients of renal transplantation are: peripheral edema, hypertriglyceridemia, hypertension, hypercholesterolemia, creatinine increased, constipation, abdominal pain, diarrhea, headache, fever, urinary tract infection, anemia, nausea, arthralgia, pain, and thrombocytopenia.

The most common (≥20%) adverse reactions observed with sirolimus in the clinical study for the treatment of LAM are: stomatitis, diarrhea, abdominal pain, nausea, nasopharyngitis, acne, chest pain, peripheral edema, upper respiratory tract infection, headache, dizziness, myalgia, and hypercholesterolemia.

The following adverse reactions resulted in a rate of discontinuation of >5% in clinical trials for renal transplant rejection prophylaxis: creatinine increased, hypertriglyceridemia, and TTP. In patients with LAM, 11% of subjects discontinued due to adverse reactions, with no single adverse reaction leading to discontinuation in more than one patient being treated with sirolimus.

6.1 Clinical Studies Experience in Prophylaxis of Organ Rejection Following Renal Transplantation

The safety and efficacy of sirolimus oral solution for the prevention of organ rejection following renal transplantation were assessed in two randomized, double-blind, multicenter, controlled trials [see Clinical Studies (14.1)]. The safety profiles in the two studies were similar.

The incidence of adverse reactions in the randomized, double-blind, multicenter, placebo-controlled trial (Study 2) in which 219 renal transplant patients received sirolimus oral solution 2 mg/day, 208 received sirolimus oral solution 5 mg/day, and 124 received placebo is presented in Table 1 below. The study population had a mean age of 46 years (range 15 to 71 years), the distribution was 67% male, and the composition by race was: White (78%), Black (11%), Asian (3%), Hispanic (2%), and Other (5%). All patients were treated with cyclosporine and corticosteroids. Data (≥ 12 months post-transplant) presented in the following table show the adverse reactions that occurred in at least one of the sirolimus treatment groups with an incidence of ≥20%.

The safety profile of the tablet did not differ from that of the oral solution formulation [see Clinical Studies (14.1)].

In general, adverse reactions related to the administration of sirolimus were dependent on dose/concentration. Although a daily maintenance dose of 5 mg, with a loading dose of 15 mg, was shown to be safe and effective, no efficacy advantage over the 2 mg dose could be established for renal transplant patients. Patients receiving 2 mg of sirolimus oral solution per day demonstrated an overall better safety profile than did patients receiving 5 mg of sirolimus oral solution per day.

Because clinical trials are conducted under widely varying conditions, adverse reaction rates observed in one clinical trial of a drug cannot be directly compared with rates in the clinical trials of the same or another drug and may not reflect the rates observed in practice.

TABLE 1: ADVERSE REACTIONS OCCURRING AT A FREQUENCY OF ≥20% IN AT LEAST ONE OF THE SIROLIMUS TREATMENT GROUPS IN A STUDY OF PROPHYLAXIS OF ORGAN REJECTION FOLLOWING RENAL TRANSPLANTATION (%) AT ≥12 MONTHS POST-TRANSPLANTATION (STUDY 2) [Patients received cyclosporine and corticosteroids.]
 | –––Sirolimus Oral Solution–––
Adverse Reaction | 2 mg/day (n = 218) | 5 mg/day (n = 208) | Placebo (n = 124)
Peripheral edema | 54 | 58 | 48
Hypertriglyceridemia | 45 | 57 | 23
Hypertension | 45 | 49 | 48
Hypercholesterolemia | 43 | 46 | 23
Creatinine increased | 39 | 40 | 38
Constipation | 36 | 38 | 31
Abdominal pain | 29 | 36 | 30
Diarrhea | 25 | 35 | 27
Headache | 34 | 34 | 31
Fever | 23 | 34 | 35
Urinary tract infection | 26 | 33 | 26
Anemia | 23 | 33 | 21
Nausea | 25 | 31 | 29
Arthralgia | 25 | 31 | 18
Thrombocytopenia | 14 | 30 | 9
Pain | 33 | 29 | 25
Acne | 22 | 22 | 19
Rash | 10 | 20 | 6
Edema | 20 | 18 | 15

The following adverse reactions were reported less frequently (≥3%, but <20%)

- Body as a Whole – Sepsis, lymphocele, herpes zoster, herpes simplex.
- Cardiovascular – Venous thromboembolism (including pulmonary embolism, deep venous thrombosis), tachycardia.
- Digestive System – Stomatitis.
- Hematologic and Lymphatic System – Thrombotic thrombocytopenic purpura/hemolytic uremic syndrome (TTP/HUS), leukopenia.
- Metabolic/Nutritional – Abnormal healing, increased lactic dehydrogenase (LDH), hypokalemia, diabetes mellitus.
- Musculoskeletal System – Bone necrosis.
- Respiratory System – Pneumonia, epistaxis.
- Skin – Melanoma, squamous cell carcinoma, basal cell carcinoma.
- Urogenital System – Pyelonephritis, decline in renal function (creatinine increased) in long-term combination of cyclosporine with sirolimus [see Warnings and Precautions (5.8)], ovarian cysts, menstrual disorders (including amenorrhea and menorrhagia).

Less frequently (<3%) occurring adverse reactions included: lymphoma/post-transplant lymphoproliferative disorder, mycobacterial infections (including M. tuberculosis), pancreatitis, cytomegalovirus (CMV), and Epstein-Barr virus.

Increased Serum Cholesterol and Triglycerides

The use of sirolimus in renal transplant patients was associated with increased serum cholesterol and triglycerides that may require treatment.

In Studies 1 and 2, in de novo renal transplant patients who began the study with fasting, total serum cholesterol <200 mg/dL or fasting, total serum triglycerides <200 mg/dL, there was an increased incidence of hypercholesterolemia (fasting serum cholesterol >240 mg/dL) or hypertriglyceridemia (fasting serum triglycerides >500 mg/dL), respectively, in patients receiving both sirolimus 2 mg and sirolimus 5 mg compared with azathioprine and placebo controls.

Treatment of new-onset hypercholesterolemia with lipid-lowering agents was required in 42–52% of patients enrolled in the sirolimus arms of Studies 1 and 2 compared with 16% of patients in the placebo arm and 22% of patients in the azathioprine arm. In other sirolimus renal transplant studies, up to 90% of patients required treatment for hyperlipidemia and hypercholesterolemia with anti-lipid therapy (e.g., statins, fibrates). Despite anti-lipid management, up to 50% of patients had fasting serum cholesterol levels >240 mg/dL and triglycerides above recommended target levels [see Warnings and Precautions (5.7)].

Abnormal Healing

Abnormal healing events following transplant surgery include fascial dehiscence, incisional hernia, and anastomosis disruption (e.g., wound, vascular, airway, ureteral, biliary).

Malignancies

Table 2 below summarizes the incidence of malignancies in the two controlled trials (Studies 1 and 2) for the prevention of acute rejection [see Clinical Studies (14.1)].

At 24 months (Study 1) and 36 months (Study 2) post-transplant, there were no significant differences among treatment groups.

TABLE 2: INCIDENCE (%) OF MALIGNANCIES IN STUDY 1 (24 MONTHS) AND STUDY 2 (36 MONTHS) POST-TRANSPLANT [Patients received cyclosporine and corticosteroids.] , [Includes patients who prematurely discontinued treatment.]
Malignancy | Sirolimus Oral Solution 2 mg/day |  | Sirolimus Oral Solution 5 mg/day |  | Azathioprine 2–3 mg/kg/day | Placebo
Malignancy | Study 1 (n = 284) | Study 2 (n = 227) | Study 1 (n = 274) | Study 2 (n = 219) | Study 1 (n = 161) | Study 2 (n = 130)
Lymphoma/lymphoproliferative disease | 0.7 | 1.8 | 1.1 | 3.2 | 0.6 | 0.8
Skin Carcinoma
Any Squamous Cell [Patients may be counted in more than one category.] | 0.4 | 2.7 | 2.2 | 0.9 | 3.8 | 3.0
Any Basal Cell | 0.7 | 2.2 | 1.5 | 1.8 | 2.5 | 5.3
Melanoma | 0.0 | 0.4 | 0.0 | 1.4 | 0.0 | 0.0
Miscellaneous/Not Specified | 0.0 | 0.0 | 0.0 | 0.0 | 0.0 | 0.8
Total | 1.1 | 4.4 | 3.3 | 4.1 | 4.3 | 7.7
Other Malignancy | 1.1 | 2.2 | 1.5 | 1.4 | 0.6 | 2.3

6.2 Sirolimus Following Cyclosporine Withdrawal

The incidence of adverse reactions was determined through 36 months in a randomized, multicenter, controlled trial (Study 3) in which 215 renal transplant patients received sirolimus as a maintenance regimen following cyclosporine withdrawal, and 215 patients received sirolimus with cyclosporine therapy [see Clinical Studies (14.2)]. All patients were treated with corticosteroids. The safety profile prior to randomization (start of cyclosporine withdrawal) was similar to that of the 2 mg sirolimus groups in Studies 1 and 2.

Following randomization (at 3 months), patients who had cyclosporine eliminated from their therapy experienced higher incidences of the following adverse reactions: abnormal liver function tests (including increased AST/SGOT and increased ALT/SGPT), hypokalemia, thrombocytopenia, and abnormal healing. Conversely, the incidence of the following adverse events was higher in patients who remained on cyclosporine than those who had cyclosporine withdrawn from therapy: hypertension, cyclosporine toxicity, increased creatinine, abnormal kidney function, toxic nephropathy, edema, hyperkalemia, hyperuricemia, and gum hyperplasia. Mean systolic and diastolic blood pressure improved significantly following cyclosporine withdrawal.

Malignancies

The incidence of malignancies in Study 3 [see Clinical Studies (14.2)] is presented in Table 3.

In Study 3, the incidence of lymphoma/lymphoproliferative disease was similar in all treatment groups. The overall incidence of malignancy was higher in patients receiving sirolimus plus cyclosporine compared with patients who had cyclosporine withdrawn. Conclusions regarding these differences in the incidence of malignancy could not be made because Study 3 was not designed to consider malignancy risk factors or systematically screen subjects for malignancy. In addition, more patients in the sirolimus with cyclosporine group had a pre-transplantation history of skin carcinoma.

TABLE 3: INCIDENCE (%) OF MALIGNANCIES IN STUDY 3 (CYCLOSPORINE WITHDRAWAL STUDY) AT 36 MONTHS POST-TRANSPLANT [Patients received cyclosporine and corticosteroids.] , [Includes patients who prematurely discontinued treatment.]
Malignancy | Nonrandomized (n = 95) | Sirolimus with Cyclosporine Therapy (n = 215) | Sirolimus Following Cyclosporine Withdrawal (n = 215)
Lymphoma/lymphoproliferative disease | 1.1 | 1.4 | 0.5
Skin Carcinoma
Any Squamous Cell [Patients may be counted in more than one category.] | 3.2 | 3.3 | 2.3
Any Basal Cell | 3.2 | 6.5 | 2.3
Melanoma | 0.0 | 0.5 | 0.0
Miscellaneous/Not Specified | 1.1 | 0.9 | 0.0
Total | 4.2 | 7.9 | 3.7
Other Malignancy | 3.2 | 3.3 | 1.9

6.3 High-Immunologic Risk Renal Transplant Patients

Safety was assessed in 224 patients who received at least one dose of sirolimus with cyclosporine [see Clinical Studies (14.3)]. Overall, the incidence and nature of adverse reactions was similar to those seen in previous combination studies with sirolimus. The incidence of malignancy was 1.3% at 12 months.

6.4 Conversion from Calcineurin Inhibitors to Sirolimus in Maintenance Renal Transplant Population

The safety and efficacy of conversion from calcineurin inhibitors to sirolimus in maintenance renal transplant population have not been established [see Clinical Studies (14.4)]. In a study evaluating the safety and efficacy of conversion from calcineurin inhibitors to sirolimus (initial target sirolimus concentrations of 12–20 ng/mL, and then 8–20 ng/mL, by chromatographic assay) in maintenance renal transplant patients, enrollment was stopped in the subset of patients (n = 87) with a baseline glomerular filtration rate of less than 40 mL/min. There was a higher rate of serious adverse events, including pneumonia, acute rejection, graft loss and death, in this stratum of the sirolimus treatment arm.

The subset of patients with a baseline glomerular filtration rate of less than 40 mL/min had 2 years of follow-up after randomization. In this population, the rate of pneumonia was 25.9% (15/58) versus 13.8% (4/29), graft loss (excluding death with functioning graft loss) was 22.4% (13/58) versus 31.0% (9/29), and death was 15.5% (9/58) versus 3.4% (1/29) in the sirolimus conversion group and CNI continuation group, respectively.

In the subset of patients with a baseline glomerular filtration rate of greater than 40 mL/min, there was no benefit associated with conversion with regard to improvement in renal function and a greater incidence of proteinuria in the sirolimus conversion arm.

Overall in this study, a 5-fold increase in the reports of tuberculosis among sirolimus 2.0% (11/551) and comparator 0.4% (1/273) treatment groups was observed with 2:1 randomization scheme.

In a second study evaluating the safety and efficacy of conversion from tacrolimus to sirolimus 3 to 5 months post-kidney transplant, a higher rate of adverse events, discontinuations due to adverse events, acute rejection, and new onset diabetes mellitus was observed following conversion to sirolimus. There was also no benefit with respect to renal function and a greater incidence of proteinuria was observed after conversion to sirolimus [see Clinical Studies (14.4)].

6.5 Pediatric Renal Transplant Patients

Safety was assessed in a controlled clinical trial in pediatric (<18 years of age) renal transplant patients considered at high-immunologic risk, defined as a history of one or more acute allograft rejection episodes and/or the presence of chronic allograft nephropathy on a renal biopsy [see Clinical Studies (14.6)]. The use of sirolimus in combination with calcineurin inhibitors and corticosteroids was associated with a higher incidence of deterioration of renal function (creatinine increased) compared to calcineurin inhibitor-based therapy, serum lipid abnormalities (including, but not limited to, increased serum triglycerides and cholesterol), and urinary tract infections.

6.6 Patients with Lymphangioleiomyomatosis

Safety was assessed in a controlled trial involving 89 patients with lymphangioleiomyomatosis, 46 of whom were treated with sirolimus [see Clinical Studies (14.7)]. The adverse drug reactions observed in this trial were consistent with the known safety profile for renal transplant patients receiving sirolimus, with the addition of weight decreased which was reported at a greater incidence with sirolimus when compared to placebo. Adverse reactions occurring at a frequency of ≥20% in the sirolimus treatment group and greater than placebo include stomatitis, diarrhea, abdominal pain, nausea, nasopharyngitis, acne, chest pain, peripheral edema, upper respiratory tract infection, headache, dizziness, myalgia, and hypercholesterolemia.

6.7 Postmarketing Experience

The following adverse reactions have been identified during post-approval use of sirolimus in transplant patients. Because these reactions are reported voluntarily from a population of uncertain size, it is not always possible to reliably estimate their frequency or establish a causal relationship to drug exposure.

- Body as a Whole – Lymphedema.
- Cardiovascular – Pericardial effusion (including hemodynamically significant effusions and tamponade requiring intervention in children and adults) and fluid accumulation.
- Digestive System – Ascites.
- Hematological/Lymphatic – Pancytopenia, neutropenia.
- Hepatobiliary Disorders – Hepatotoxicity, including fatal hepatic necrosis, with elevated sirolimus trough concentrations.
- Immune System – Hypersensitivity reactions, including anaphylactic/anaphylactoid reactions, angioedema, and hypersensitivity vasculitis [see Warnings and Precautions (5.4)].
- Infections – Tuberculosis. BK virus associated nephropathy has been observed in patients receiving immunosuppressants, including sirolimus. This infection may be associated with serious outcomes, including deteriorating renal function and renal graft loss. Cases of progressive multifocal leukoencephalopathy (PML), sometimes fatal, have been reported in patients treated with immunosuppressants, including sirolimus [see Warnings and Precautions (5.10)]. Clostridium difficile enterocolitis.
- Metabolic/Nutritional – Liver function test abnormal, AST/SGOT increased, ALT/SGPT increased, hypophosphatemia, hyperglycemia, diabetes mellitus.
- Nervous System - Posterior reversible encephalopathy syndrome.
- Respiratory – Cases of interstitial lung disease (including pneumonitis, bronchiolitis obliterans organizing pneumonia [BOOP], and pulmonary fibrosis), some fatal, with no identified infectious etiology have occurred in patients receiving immunosuppressive regimens including sirolimus. In some cases, the interstitial lung disease has resolved upon discontinuation or dose reduction of sirolimus. The risk may be increased as the sirolimus trough concentration increases [see Warnings and Precautions (5.11)]; pulmonary hemorrhage; pleural effusion; alveolar proteinosis.
- Skin – Neuroendocrine carcinoma of the skin (Merkel cell carcinoma) [see Warnings and Precautions (5.18)], exfoliative dermatitis [see Warnings and Precautions (5.4)].
- Urogenital – Nephrotic syndrome, proteinuria, focal segmental glomerulosclerosis, ovarian cysts, menstrual disorders (including amenorrhea and menorrhagia). Azoospermia has been reported with the use of sirolimus and has been reversible upon discontinuation of sirolimus in most cases.

7 DRUG INTERACTIONS

Sirolimus is known to be a substrate for both cytochrome P-450 3A4 (CYP3A4) and p-glycoprotein (P-gp). Inducers of CYP3A4 and P-gp may decrease sirolimus concentrations whereas inhibitors of CYP3A4 and P-gp may increase sirolimus concentrations.

7.1 Use with Cyclosporine

Cyclosporine, a substrate and inhibitor of CYP3A4 and P-gp, was demonstrated to increase sirolimus concentrations when co-administered with sirolimus. In order to diminish the effect of this interaction with cyclosporine, it is recommended that sirolimus be taken 4 hours after administration of cyclosporine oral solution (MODIFIED) and/or cyclosporine capsules (MODIFIED). If cyclosporine is withdrawn from combination therapy with sirolimus, higher doses of sirolimus are needed to maintain the recommended sirolimus trough concentration ranges [see Dosage and Administration (2.2), Clinical Pharmacology (12.3)].

7.2 Strong Inducers and Strong Inhibitors of CYP3A4 and P-gp

Avoid concomitant use of sirolimus with strong inducers (e.g., rifampin, rifabutin) and strong inhibitors (e.g., ketoconazole, voriconazole, itraconazole, erythromycin, telithromycin, clarithromycin) of CYP3A4 and P-gp. Alternative agents with lesser interaction potential with sirolimus should be considered [see Warnings and Precautions (5.20), Clinical Pharmacology (12.3)].

7.3 Grapefruit Juice

Because grapefruit juice inhibits the CYP3A4-mediated metabolism of sirolimus, it must not be taken with or be used for dilution of sirolimus [see Dosage and Administration (2.9), Drug Interactions (7.3), Clinical Pharmacology (12.3)].

7.4 Weak and Moderate Inducers or Inhibitors of CYP3A4 and P-gp

Exercise caution when using sirolimus with drugs or agents that are modulators of CYP3A4 and P-gp. The dosage of sirolimus and/or the co-administered drug may need to be adjusted [see Clinical Pharmacology (12.3)].

- Drugs that could increase sirolimus blood concentrations:
  Bromocriptine, cimetidine, cisapride, clotrimazole, danazol, diltiazem, fluconazole, letermovir, protease inhibitors (e.g., HIV and hepatitis C that include drugs such as ritonavir, indinavir, boceprevir, and telaprevir), metoclopramide, nicardipine, troleandomycin, verapamil
- Drugs and other agents that could decrease sirolimus concentrations:
  Carbamazepine, phenobarbital, phenytoin, rifapentine, St. John's Wort (Hypericum perforatum)
- Drugs with concentrations that could increase when given with sirolimus:
  Verapamil.

7.5 Cannabidiol

The blood levels of sirolimus may increase upon concomitant use with cannabidiol. When cannabidiol and sirolimus are co-administered, closely monitor for an increase in sirolimus blood levels and for adverse reactions suggestive of sirolimus toxicity. A dose reduction of sirolimus should be considered as needed when sirolimus is co-administered with cannabidiol [see Dosage and Administration (2.5), Warnings and Precautions (5.21)].

8 USE IN SPECIFIC POPULATIONS

8.1 Pregnancy

Risk Summary

Based on animal studies and the mechanism of action, sirolimus can cause fetal harm when administered to a pregnant woman [see Data, Clinical Pharmacology (12.1)]. There are limited data on the use of sirolimus during pregnancy; however, these data are insufficient to inform a drug-associated risk of adverse developmental outcomes. In animal studies, sirolimus was embryo/fetotoxic in rats at sub-therapeutic doses [see Data]. Advise pregnant women of the potential risk to a fetus.

The estimated background risk of major birth defects and miscarriage for the indicated population is unknown. In the U.S. general population, the estimated background risk of major birth defects and miscarriage in clinically recognized pregnancies is 2–4% and 15–20%, respectively.

Data

Animal Data

Sirolimus crossed the placenta and was toxic to the conceptus.

In rat embryo-fetal development studies, pregnant rats were administered sirolimus orally during the period of organogenesis (Gestational Day 6–15). Sirolimus produced embryo-fetal lethality at 0.5 mg/kg (2.5-fold the clinical dose of 2 mg, on a body surface area basis) and reduced fetal weight at 1 mg/kg (5-fold the clinical dose of 2 mg). The no observed adverse effect level (NOAEL) for fetal toxicity in rats was 0.1 mg/kg (0.5-fold the clinical dose of 2 mg). Maternal toxicity (weight loss) was observed at 2 mg/kg (10-fold the clinical dose of 2 mg). The NOAEL for maternal toxicity was 1 mg/kg. In combination with cyclosporine, rats had increased embryo-fetal mortality compared with sirolimus alone.

In rabbit embryo-fetal development studies, pregnant rabbits were administered sirolimus orally during the period of organogenesis (Gestational Day 6–18). There were no effects on embryo-fetal development at doses up to 0.05 mg/kg (0.5-fold the clinical dose of 2 mg, on a body surface area basis); however, at doses of 0.05 mg/kg and above, the ability to sustain a successful pregnancy was impaired (i.e., embryo-fetal abortion or early resorption). Maternal toxicity (decreased body weight) was observed at 0.05 mg/kg. The NOAEL for maternal toxicity was 0.025 mg/kg (0.25-fold the clinical dose of 2 mg).

In a pre- and post-natal development study in rats, pregnant females were dosed during gestation and lactation (Gestational Day 6 through Lactation Day 20). An increased incidence of dead pups, resulting in reduced live litter size, occurred at 0.5 mg/kg (2.5-fold the clinical dose of 2 mg/kg on a body surface area basis). At 0.1 mg/kg (0.5-fold the clinical dose of 2 mg), there were no adverse effects on offspring. Sirolimus did not cause maternal toxicity or affect developmental parameters in the surviving offspring (morphological development, motor activity, learning, or fertility assessment) at 0.5 mg/kg, the highest dose tested.

8.2 Lactation

Risk Summary

It is not known whether sirolimus is present in human milk. There are no data on its effects on the breastfed infant or milk production. The pharmacokinetic and safety profiles of sirolimus in infants are not known. Sirolimus is present in the milk of lactating rats. There is potential for serious adverse effects from sirolimus in breastfed infants based on mechanism of action [see Clinical Pharmacology (12.1)]. The developmental and health benefits of breastfeeding should be considered along with the mother's clinical need for sirolimus and any potential adverse effects on the breastfed child from sirolimus.

8.3 Females and Males of Reproductive Potential

Contraception

Females should not be pregnant or become pregnant while receiving sirolimus. Advise females of reproductive potential that animal studies have been shown sirolimus to be harmful to the developing fetus. Females of reproductive potential are recommended to use highly effective contraceptive method. Effective contraception must be initiated before sirolimus therapy, during sirolimus therapy, and for 12 weeks after sirolimus therapy has been stopped [see Warnings and Precautions (5.15), Use in Specific Populations (8.1)].

Infertility

Based on clinical findings and findings in animals, male and female fertility may be compromised by the treatment with sirolimus [see Adverse Reactions (6.7), Nonclinical Toxicology (13.1)]. Ovarian cysts and menstrual disorders (including amenorrhea and menorrhagia) have been reported in females with the use of sirolimus. Azoospermia has been reported in males with the use of sirolimus and has been reversible upon discontinuation of sirolimus in most cases.

8.4 Pediatric Use

Renal Transplant

The safety and efficacy of sirolimus in pediatric patients <13 years have not been established.

The safety and efficacy of sirolimus oral solution and sirolimus tablets have been established for prophylaxis of organ rejection in renal transplantation in children ≥13 years judged to be at low- to moderate-immunologic risk. Use of sirolimus oral solution and sirolimus tablets in this subpopulation of children ≥13 years is supported by evidence from adequate and well-controlled trials of sirolimus oral solution in adults with additional pharmacokinetic data in pediatric renal transplantation patients [see Clinical Pharmacology (12.3)].

Safety and efficacy information from a controlled clinical trial in pediatric and adolescent (<18 years of age) renal transplant patients judged to be at high-immunologic risk, defined as a history of one or more acute rejection episodes and/or the presence of chronic allograft nephropathy, do not support the chronic use of sirolimus oral solution or tablets in combination with calcineurin inhibitors and corticosteroids, due to the higher incidence of lipid abnormalities and deterioration of renal function associated with these immunosuppressive regimens compared to calcineurin inhibitors, without increased benefit with respect to acute rejection, graft survival, or patient survival [see Clinical Studies (14.6)].

Lymphangioleiomyomatosis

The safety and efficacy of Sirolimus in pediatric patients <18 years have not been established.

8.5 Geriatric Use

Clinical studies of sirolimus oral solution or tablets did not include sufficient numbers of patients ≥65 years to determine whether they respond differently from younger patients. Data pertaining to sirolimus trough concentrations suggest that dose adjustments based upon age in geriatric renal patients are not necessary. Differences in responses between the elderly and younger patients have not been identified. In general, dose selection for an elderly patient should be cautious, usually starting at the low end of the dosing range, reflecting the greater frequency of decreased hepatic, or cardiac function, and of concomitant disease or other drug therapy.

8.6 Patients with Hepatic Impairment

The maintenance dose of sirolimus should be reduced in patients with hepatic impairment [see Dosage and Administration (2.7), Clinical Pharmacology (12.3)].

8.7 Patients with Renal Impairment

Dosage adjustment is not required in patients with renal impairment [see Dosage and Administration (2.8), Clinical Pharmacology (12.3)].

10 OVERDOSAGE

Reports of overdose with sirolimus have been received; however, experience has been limited. In general, the adverse effects of overdose are consistent with those listed in the adverse reactions section [see Adverse Reactions (6)].

General supportive measures should be followed in all cases of overdose. Based on the low aqueous solubility and high erythrocyte and plasma protein binding of sirolimus, it is anticipated that sirolimus is not dialyzable to any significant extent. In mice and rats, the acute oral LD50 was greater than 800 mg/kg.

11 DESCRIPTION

Sirolimus is an mTOR inhibitor immunosuppressive agent. Sirolimus is a macrocyclic lactone produced by Streptomyces hygroscopicus. The chemical name of sirolimus (also known as rapamycin) is (3S,6R,7E,9R,10R,12R,14S,15E,17E,19E,21S,23S,26R,27R,34aS)-9,10,12,13,14,21,22,23,24,25,26,27,32,33,34, 34a-hexadecahydro-9,27-dihydroxy-3-[(1R)-2-[(1S,3R,4R)-4-hydroxy-3-methoxycyclohexyl]-1-methylethyl]-10,21-dimethoxy-6,8,12,14,20,26-hexamethyl-23,27-epoxy-3H-pyrido[2,1-c][1,4] oxaazacyclohentriacontine-1,5,11,28,29 (4H,6H,31H)-pentone. Its molecular formula is C51H79NO13 and its molecular weight is 914.2. The structural formula of sirolimus is illustrated as follows.

Sirolimus is a white to off-white powder and is insoluble in water, but freely soluble in benzyl alcohol, chloroform, acetone, and acetonitrile.

Sirolimus is available for administration as an oral solution containing 1 mg/mL sirolimus.

The inactive ingredients in sirolimus oral solution are Phosal 50 PG® (phosphatidylcholine, propylene glycol, mono- and di-glycerides, ethanol, soy fatty acids, and ascorbyl palmitate) and polysorbate 80. Sirolimus oral solution contains 1.5% – 2.5% ethanol.

12 CLINICAL PHARMACOLOGY

12.1 Mechanism of Action

Sirolimus inhibits T-lymphocyte activation and proliferation that occurs in response to antigenic and cytokine (Interleukin [IL]-2, IL-4, and IL-15) stimulation by a mechanism that is distinct from that of other immunosuppressants. Sirolimus also inhibits antibody production. In cells, sirolimus binds to the immunophilin, FK Binding Protein-12 (FKBP-12), to generate an immunosuppressive complex. The sirolimus:FKBP-12 complex has no effect on calcineurin activity. This complex binds to and inhibits the activation of the mammalian target of rapamycin (mTOR), a key regulatory kinase. This inhibition suppresses cytokine-driven T-cell proliferation, inhibiting the progression from the G1 to the S phase of the cell cycle.

Mammalian target of rapamycin (mTOR) inhibitors such as sirolimus have been shown in vitro to inhibit production of certain growth factors that may affect angiogenesis, fibroblast proliferation, and vascular permeability.

Studies in experimental models show that sirolimus prolongs allograft (kidney, heart, skin, islet, small bowel, pancreatico-duodenal, and bone marrow) survival in mice, rats, pigs, and/or primates. Sirolimus reverses acute rejection of heart and kidney allografts in rats and prolongs the graft survival in presensitized rats. In some studies, the immunosuppressive effect of sirolimus lasts up to 6 months after discontinuation of therapy. This tolerization effect is alloantigen-specific.

In rodent models of autoimmune disease, sirolimus suppresses immune-mediated events associated with systemic lupus erythematosus, collagen-induced arthritis, autoimmune type I diabetes, autoimmune myocarditis, experimental allergic encephalomyelitis, graft-versus-host disease, and autoimmune uveoretinitis.

Lymphangioleiomyomatosis involves lung tissue infiltration with smooth muscle-like cells that harbor inactivating mutations of the tuberous sclerosis complex (TSC) gene (LAM cells). Loss of TSC gene function activates the mTOR signaling pathway, resulting in cellular proliferation and release of lymphangiogenic growth factors. Sirolimus inhibits the activated mTOR pathway and thus the proliferation of LAM cells.

12.2 Pharmacodynamics

Orally-administered sirolimus, at doses of 2 mg/day and 5 mg/day, significantly reduced the incidence of organ rejection in low- to moderate-immunologic risk renal transplant patients at 6 months following transplantation compared with either azathioprine or placebo [see Clinical Studies (14.1)]. There was no demonstrable efficacy advantage of a daily maintenance dose of 5 mg with a loading dose of 15 mg over a daily maintenance dose of 2 mg with a loading dose of 6 mg. Therapeutic drug monitoring should be used to maintain sirolimus drug levels within the target-range [see Dosage and Administration (2.5)].

12.3 Pharmacokinetics

Sirolimus pharmacokinetics activity have been determined following oral administration in healthy subjects, pediatric patients, hepatically impaired patients, and renal transplant patients.

The pharmacokinetic parameters of sirolimus in low- to moderate-immunologic risk adult renal transplant patients following multiple dosing with sirolimus 2 mg daily, in combination with cyclosporine and corticosteroids, is summarized in Table 4.

TABLE 4: MEAN ± SD STEADY STATE SIROLIMUS PHARMACOKINETIC PARAMETERS IN LOW- TO MODERATE-IMMUNOLOGIC RISK ADULT RENAL TRANSPLANT PATIENTS FOLLOWING SIROLIMUS 2 MG DAILY [In presence of cyclosporine administered 4 hours before sirolimus dosing.] , [Based on data collected at months 1 and 3 post-transplantation.]
 | Multiple Dose (daily dose)
 | Solution | Tablets
Cmax (ng/mL) | 14.4 ± 5.3 | 15.0 ± 4.9
tmax (hr) | 2.1 ± 0.8 | 3.5 ± 2.4
AUC (ng∙h/mL) | 194 ± 78 | 230 ± 67
Cmin (ng/mL) [Average Cmin over 6 months.] | 7.1 ± 3.5 | 7.6 ± 3.1
CL/F (mL/h/kg) | 173 ± 50 | 139 ± 63

Whole blood trough sirolimus concentrations, as measured by LC/MS/MS in renal transplant patients, were significantly correlated with AUCτ,ss. Upon repeated, twice-daily administration without an initial loading dose in a multiple-dose study, the average trough concentration of sirolimus increases approximately 2- to 3-fold over the initial 6 days of therapy, at which time steady-state is reached. A loading dose of 3 times the maintenance dose will provide near steady-state concentrations within 1 day in most patients [see Dosage and Administration (2.3, 2.5), Warning and Precautions (5.17)].

Absorption

Following administration of sirolimus oral solution, the mean times to peak concentration (tmax) of sirolimus are approximately 1 hour and 2 hours in healthy subjects and renal transplant patients, respectively. The systemic availability of sirolimus is low, and was estimated to be approximately 14% after the administration of sirolimus oral solution. In healthy subjects, the mean bioavailability of sirolimus after administration of the tablet is approximately 27% higher relative to the solution. Sirolimus tablets are not bioequivalent to the solution; however, clinical equivalence has been demonstrated at the 2 mg dose level. Sirolimus concentrations, following the administration of sirolimus oral solution to stable renal transplant patients, are dose-proportional between 3 and 12 mg/m^2.

Food Effects

To minimize variability in sirolimus concentrations, both sirolimus oral solution and tablets should be taken consistently with or without food [see Dosage and Administration (2)]. In healthy subjects, a high-fat meal (861.8 kcal, 54.9% kcal from fat) increased the mean total exposure (AUC) of sirolimus by 23 to 35%, compared with fasting. The effect of food on the mean sirolimus Cmax was inconsistent depending on the sirolimus dosage form evaluated.

Distribution

The mean (± SD) blood-to-plasma ratio of sirolimus was 36 ± 18 in stable renal allograft patients, indicating that sirolimus is extensively partitioned into formed blood elements. The mean volume of distribution (Vss/F) of sirolimus is 12 ± 8 L/kg. Sirolimus is extensively bound (approximately 92%) to human plasma proteins, mainly serum albumin (97%), α1-acid glycoprotein, and lipoproteins.

Metabolism

Sirolimus is a substrate for both CYP3A4 and P-gp. Sirolimus is extensively metabolized in the intestinal wall and liver and undergoes counter-transport from enterocytes of the small intestine into the gut lumen. Inhibitors of CYP3A4 and P-gp increase sirolimus concentrations. Inducers of CYP3A4 and P-gp decrease sirolimus concentrations [see Warnings and Precautions (5.20) and Drug Interactions (7)]. Sirolimus is extensively metabolized by O-demethylation and/or hydroxylation. Seven (7) major metabolites, including hydroxy, demethyl, and hydroxydemethyl, are identifiable in whole blood. Some of these metabolites are also detectable in plasma, fecal, and urine samples. Sirolimus is the major component in human whole blood and contributes to more than 90% of the immunosuppressive activity.

Excretion

After a single dose of [^14C] sirolimus oral solution in healthy volunteers, the majority (91%) of radioactivity was recovered from the feces, and only a minor amount (2.2%) was excreted in urine. The mean ± SD terminal elimination half-life (t½) of sirolimus after multiple dosing in stable renal transplant patients was estimated to be about 62 ± 16 hours.

Sirolimus Concentrations (Chromatographic Equivalent) Observed in Phase 3 Clinical Studies

The following sirolimus concentrations (chromatographic equivalent) were observed in phase 3 clinical studies for prophylaxis of organ rejection in de novo renal transplant patients [see Clinical Studies (14)].

TABLE 5: SIROLIMUS WHOLE BLOOD TROUGH CONCENTRATIONS OBSERVED IN RENAL TRANSPLANT PATIENTS ENROLLED IN PHASE 3 STUDIES
Patient Population(Study number) | Treatment | Year 1 |  | Year 3
Patient Population(Study number) | Treatment | Mean (ng/mL) | 10th – 90th percentiles (ng/mL) | Mean (ng/mL) | 10th – 90th percentiles (ng/mL)
Low-to-moderate risk (Studies 1 & 2) | Sirolimus (2 mg/day) + CsA | 7.2 | 3.6 – 11 | – | –
Low-to-moderate risk (Studies 1 & 2) | Sirolimus (5 mg/day) + CsA | 14 | 8 – 22 | – | –
Low-to-moderate risk (Study 3) | Sirolimus + CsA | 8.6 | 5 – 13 [Months 4 through 12] | 9.1 | 5.4 – 14
Low-to-moderate risk (Study 3) | Sirolimus alone | 19 | 14 – 22 | 16 | 11 – 22
High risk (Study 4) | Sirolimus + CsA | 15.7 11.8 11.5 | 5.4 – 27.3 [Up to Week 2; observed CsA Cmin was 217 (56 – 432) ng/mL] 6.2 – 16.9 [Week 2 to Week 26; observed CsA Cmin range was 174 (71 – 288) ng/mL] 6.3 – 17.3 [Week 26 to Week 52; observed CsA Cmin was 136 (54.5 – 218) ng/mL] | – | –

The withdrawal of cyclosporine and concurrent increases in sirolimus trough concentrations to steady-state required approximately 6 weeks. Following cyclosporine withdrawal, larger sirolimus doses were required due to the absence of the inhibition of sirolimus metabolism and transport by cyclosporine and to achieve higher target sirolimus trough concentrations during concentration-controlled administration [see Dosage and Administration (2.1), Drug Interactions (7.1)].

Lymphangioleiomyomatosis

In a clinical trial of patients with lymphangioleiomyomatosis, the median whole blood sirolimus trough concentration after 3 weeks of receiving sirolimus tablets at a dose of 2 mg/day was 6.8 ng/mL (interquartile range 4.6 to 9.0 ng/mL; n = 37).

Pharmacokinetics in Specific Populations

Hepatic Impairment

Sirolimus was administered as a single, oral dose to subjects with normal hepatic function and to patients with Child-Pugh classification A (mild), B (moderate), or C (severe) hepatic impairment. Compared with the values in the normal hepatic function group, the patients with mild, moderate, and severe hepatic impairment had 43%, 94%, and 189% higher mean values for sirolimus AUC, respectively, with no statistically significant differences in mean Cmax. As the severity of hepatic impairment increased, there were steady increases in mean sirolimus t1/2, and decreases in the mean sirolimus clearance normalized for body weight (CL/F/kg).

The maintenance dose of sirolimus should be reduced by approximately one third in patients with mild to moderate hepatic impairment and by approximately one half in patients with severe hepatic impairment [see Dosage and Administration (2.5)]. It is not necessary to modify the sirolimus loading dose in patients with mild, moderate, and severe hepatic impairment. Therapeutic drug monitoring is necessary in all patients with hepatic impairment [see Dosage and Administration (2.7)].

Renal Impairment

The effect of renal impairment on the pharmacokinetics of sirolimus is not known. However, there is minimal (2.2%) renal excretion of the drug or its metabolites in healthy volunteers. The loading and the maintenance doses of sirolimus need not be adjusted in patients with renal impairment [see Dosage and Administration (2.6)].

Pediatric Renal Transplant Patients

Sirolimus pharmacokinetic data were collected in concentration-controlled trials of pediatric renal transplant patients who were also receiving cyclosporine and corticosteroids. The target ranges for trough concentrations were either 10–20 ng/mL for the 21 children receiving tablets, or 5–15 ng/mL for the one child receiving oral solution. The children aged 6–11 years (n = 8) received mean ± SD doses of 1.75 ± 0.71 mg/day (0.064 ± 0.018 mg/kg, 1.65 ± 0.43 mg/m^2). The children aged 12–18 years (n = 14) received mean ± SD doses of 2.79 ± 1.25 mg/day (0.053 ± 0.0150 mg/kg, 1.86 ± 0.61 mg/m^2). At the time of sirolimus blood sampling for pharmacokinetic evaluation, the majority (80%) of these pediatric patients received the sirolimus dose at 16 hours after the once-daily cyclosporine dose. See Table 6 below.

TABLE 6: SIROLIMUS PHARMACOKINETIC PARAMETERS (MEAN ± SD) IN PEDIATRIC RENAL TRANSPLANT PATIENTS (MULTIPLE-DOSE CONCENTRATION CONTROL) [Sirolimus co-administered with cyclosporine oral solution [MODIFIED] (e.g., Neoral® Oral Solution) and/or cyclosporine capsules [MODIFIED] (e.g., Neoral® Soft Gelatin Capsules).] , [As measured by Liquid Chromatographic/Tandem Mass Spectrometric Method (LC/MS/MS)]
Age (y) | n | Body weight (kg) | Cmax,ss (ng/mL) | tmax,ss (h) | Cmin,ss (ng/mL) | AUCт,ss (ng∙h/mL) | CL/F [Oral-dose clearance adjusted by either body weight (kg) or body surface area (m^2).] (mL/h/kg) | CL/F (L/h/m^2)
6–11 | 8 | 27 ± 10 | 22.1 ± 8.9 | 5.88 ± 4.05 | 10.6 ± 4.3 | 356 ± 127 | 214 ± 129 | 5.4 ± 2.8
12–18 | 14 | 52 ± 15 | 34.5 ± 12.2 | 2.7 ± 1.5 | 14.7 ± 8.6 | 466 ± 236 | 136 ± 57 | 4.7 ± 1.9

Table 7 below summarizes pharmacokinetic data obtained in pediatric dialysis patients with chronically impaired renal function.

TABLE 7: SIROLIMUS PHARMACOKINETIC PARAMETERS (MEAN ± SD) IN PEDIATRIC PATIENTS WITH END-STAGE KIDNEY DISEASE MAINTAINED ON HEMODIALYSIS OR PERITONEAL DIALYSIS (1, 3, 9, 15 mg/m^2 SINGLE DOSE) [All subjects received sirolimus oral solution.]
Age Group (y) | n | tmax (h) | t1/2 (h) | CL/F/WT (mL/h/kg)
5–11 | 9 | 1.1 ± 0.5 | 71 ± 40 | 580 ± 450
12–18 | 11 | 0.79 ± 0.17 | 55 ± 18 | 450 ± 232

Geriatric

Clinical studies of sirolimus did not include a sufficient number of patients >65 years of age to determine whether they will respond differently than younger patients. After the administration of sirolimus oral solution or tablets, sirolimus trough concentration data in renal transplant patients >65 years of age were similar to those in the adult population 18 to 65 years of age.

Gender

Sirolimus clearance in males was 12% lower than that in females; male subjects had a significantly longer t1/2 than did female subjects (72.3 hours versus 61.3 hours). Dose adjustments based on gender are not recommended.

Race

In the phase 3 trials for the prophylaxis of organ rejection following renal transplantation using sirolimus solution or tablets and cyclosporine oral solution [MODIFIED] (e.g., Neoral® Oral Solution) and/or cyclosporine capsules [MODIFIED] (e.g., Neoral® Soft Gelatin Capsules) [see Clinical Studies (14)], there were no significant differences in mean trough sirolimus concentrations over time between Black (n = 190) and non-Black (n = 852) patients during the first 6 months after transplantation.

Drug-Drug Interactions

Sirolimus is known to be a substrate for both cytochrome CYP3A4 and P-gp. The pharmacokinetic interaction between sirolimus and concomitantly administered drugs is discussed below. Drug interaction studies have not been conducted with drugs other than those described below.

Cyclosporine: Cyclosporine is a substrate and inhibitor of CYP3A4 and P-gp. Sirolimus should be taken 4 hours after administration of cyclosporine oral solution (MODIFIED) and/or cyclosporine capsules (MODIFIED). Sirolimus concentrations may decrease when cyclosporine is discontinued, unless the sirolimus dose is increased [see Dosage and Administration (2.2), Drug Interactions (7.1)].

In a single-dose drug-drug interaction study, 24 healthy volunteers were administered 10 mg sirolimus tablets either simultaneously or 4 hours after a 300-mg dose of Neoral® Soft Gelatin Capsules (cyclosporine capsules [MODIFIED]). For simultaneous administration, mean Cmax and AUC were increased by 512% and 148%, respectively, relative to administration of sirolimus alone. However, when given 4 hours after cyclosporine administration, sirolimus Cmax and AUC were both increased by only 33% compared with administration of sirolimus alone.

In a single dose drug-drug interaction study, 24 healthy volunteers were administered 10 mg sirolimus oral solution either simultaneously or 4 hours after a 300 mg dose of Neoral® Soft Gelatin Capsules (cyclosporine capsules [MODIFIED]). For simultaneous administration, the mean Cmax and AUC of sirolimus, following simultaneous administration were increased by 116% and 230%, respectively, relative to administration of sirolimus alone. However, when given 4 hours after Neoral® Soft Gelatin Capsules (cyclosporine capsules [MODIFIED]) administration, sirolimus Cmax and AUC were increased by only 37% and 80%, respectively, compared with administration of sirolimus alone.

In a single-dose cross-over drug-drug interaction study, 33 healthy volunteers received 5 mg sirolimus oral solution alone, 2 hours before, and 2 hours after a 300 mg dose of Neoral® Soft Gelatin Capsules (cyclosporine capsules [MODIFIED]). When given 2 hours before Neoral® Soft Gelatin Capsules (cyclosporine capsules [MODIFIED]) administration, sirolimus Cmax and AUC were comparable to those with administration of sirolimus alone. However, when given 2 hours after, the mean Cmax and AUC of sirolimus were increased by 126% and 141%, respectively, relative to administration of sirolimus alone.

Mean cyclosporine Cmax and AUC were not significantly affected when sirolimus oral solution was given simultaneously or when administered 4 hours after Neoral® Soft Gelatin Capsules (cyclosporine capsules [MODIFIED]). However, after multiple-dose administration of sirolimus given 4 hours after Neoral® in renal post-transplant patients over 6 months, cyclosporine oral-dose clearance was reduced, and lower doses of Neoral® Soft Gelatin Capsules (cyclosporine capsules [MODIFIED]) were needed to maintain target cyclosporine concentration.

In a multiple-dose study in 150 psoriasis patients, sirolimus 0.5, 1.5, and 3 mg/m^2/day was administered simultaneously with Sandimmune® Oral Solution (cyclosporine Oral Solution) 1.25 mg/kg/day. The increase in average sirolimus trough concentrations ranged between 67% to 86% relative to when sirolimus was administered without cyclosporine. The intersubject variability (% CV) for sirolimus trough concentrations ranged from 39.7% to 68.7%. There was no significant effect of multiple-dose sirolimus on cyclosporine trough concentrations following Sandimmune® Oral Solution (cyclosporine oral solution) administration. However, the % CV was higher (range 85.9% – 165%) than those from previous studies.

Diltiazem: Diltiazem is a substrate and inhibitor of CYP3A4 and P-gp; sirolimus concentrations should be monitored and a dose adjustment may be necessary [see Drug Interactions (7.4)]. The simultaneous oral administration of 10 mg of sirolimus oral solution and 120 mg of diltiazem to 18 healthy volunteers significantly affected the bioavailability of sirolimus. Sirolimus Cmax, tmax, and AUC were increased 1.4-, 1.3-, and 1.6-fold, respectively. Sirolimus did not affect the pharmacokinetics of either diltiazem or its metabolites desacetyldiltiazem and desmethyldiltiazem.

Erythromycin: Erythromycin is a substrate and inhibitor of CYP3A4 and P-gp; co-administration of sirolimus oral solution or tablets and erythromycin is not recommended [see Warnings and Precautions (5.20), Drug Interactions (7.2)]. The simultaneous oral administration of 2 mg daily of sirolimus oral solution and 800 mg q 8h of erythromycin as erythromycin ethylsuccinate tablets at steady state to 24 healthy volunteers significantly affected the bioavailability of sirolimus and erythromycin. Sirolimus Cmax and AUC were increased 4.4- and 4.2-fold respectively and tmax was increased by 0.4 hr. Erythromycin Cmax and AUC were increased 1.6- and 1.7-fold, respectively, and tmax was increased by 0.3 hr.

Ketoconazole: Ketoconazole is a strong inhibitor of CYP3A4 and P-gp; co-administration of sirolimus oral solution or tablets and ketoconazole is not recommended [see Warnings and Precautions (5.20), Drug Interactions (7.2)]. Multiple-dose ketoconazole administration significantly affected the rate and extent of absorption and sirolimus exposure after administration of sirolimus oral solution, as reflected by increases in sirolimus Cmax, tmax, and AUC of 4.3-fold, 38%, and 10.9-fold, respectively. However, the terminal t½ of sirolimus was not changed. Single-dose sirolimus did not affect steady-state 12-hour plasma ketoconazole concentrations.

Rifampin: Rifampin is a strong inducer of CYP3A4 and P-gp; co-administration of sirolimus oral solution or tablets and rifampin is not recommended. In patients where rifampin is indicated, alternative therapeutic agents with less enzyme induction potential should be considered [see Warnings and Precautions (5.20), Drug Interactions (7.2)]. Pretreatment of 14 healthy volunteers with multiple doses of rifampin, 600 mg daily for 14 days, followed by a single 20 mg dose of sirolimus oral solution, greatly decreased sirolimus AUC and Cmax by about 82% and 71%, respectively.

Verapamil: Verapamil is a substrate and inhibitor of CYP3A4 and P-gp; sirolimus concentrations should be monitored and a dose adjustment may be necessary; [see Drug Interactions (7.4)]. The simultaneous oral administration of 2 mg daily of sirolimus oral solution and 180 mg q 12h of verapamil at steady state to 25 healthy volunteers significantly affected the bioavailability of sirolimus and verapamil. Sirolimus Cmax and AUC were increased 2.3- and 2.2-fold, respectively, without substantial change in tmax. The Cmax and AUC of the pharmacologically active S(-) enantiomer of verapamil were both increased 1.5-fold and tmax was decreased by 1.2 hr.

Drugs Which May Be Co-administered Without Dose Adjustment

Clinically significant pharmacokinetic drug-drug interactions were not observed in studies of drugs listed below. Sirolimus and these drugs may be co-administered without dose adjustments.

- Acyclovir
- Atorvastatin
- Digoxin
- Glyburide
- Nifedipine
- Norgestrel/ethinyl estradiol (Lo/Ovral®)
- Prednisolone
- Sulfamethoxazole/trimethoprim (Bactrim®)

Other Drug-Drug Interactions

Co-administration of sirolimus with other known strong inhibitors of CYP3A4 and/or P-gp (such as voriconazole, itraconazole, telithromycin, or clarithromycin) or other known strong inducers of CYP3A4 and/or P-gp (such as rifabutin) is not recommended [see Warnings and Precautions (5.20), Drug Interactions (7.2)]. In patients in whom strong inhibitors or inducers of CYP3A4 are indicated, alternative therapeutic agents with less potential for inhibition or induction of CYP3A4 should be considered.

Care should be exercised when drugs or other substances that are substrates and/or inhibitors or inducers of CYP3A4 are administered concomitantly with sirolimus. Other drugs that have the potential to increase sirolimus blood concentrations include (but are not limited to):

- Calcium channel blockers: nicardipine.
- Antifungal agents: clotrimazole, fluconazole.
- Antibiotics: troleandomycin.
- Gastrointestinal prokinetic agents: cisapride, metoclopramide.
- Other drugs: bromocriptine, cimetidine, danazol, letermovir, protease inhibitors (e.g., for HIV and hepatitis C that include drugs such as ritonavir, indinavir, boceprevir, and telaprevir).

Other drugs that have the potential to decrease sirolimus concentrations include (but are not limited to):

- Anticonvulsants: carbamazepine, phenobarbital, phenytoin.
- Antibiotics: rifapentine.

Other Drug-Food Interactions

Grapefruit juice reduces CYP3A4-mediated drug metabolism. Grapefruit juice must not be taken with or used for dilution of sirolimus [see Dosage and Administration (2.9), Drug Interactions (7.3)].

Drug-Herb Interactions

St. John's Wort (Hypericum perforatum) induces CYP3A4 and P-gp. Since sirolimus is a substrate for both cytochrome CYP3A4 and P-gp, there is the potential that the use of St. John's Wort in patients receiving sirolimus could result in reduced sirolimus concentrations [see Drug Interactions (7.4)].

13 NONCLINICAL TOXICOLOGY

13.1 Carcinogenesis, Mutagenesis, Impairment of Fertility

Carcinogenicity studies were conducted in mice and rats. In an 86-week female mouse study at sirolimus doses 30 to 120 times higher than the 2 mg daily clinical dose (adjusted for body surface area), there was a statistically significant increase in malignant lymphoma at all dose levels compared with controls. In a second mouse study at dosages that were approximately 3 to 16 times the clinical dose (adjusted for body surface area), hepatocellular adenoma and carcinoma in males were considered sirolimus-related. In the 104-week rat study at dosages equal to or lower than the clinical dose of 2 mg daily (adjusted for body surface area), there were no significant findings.

Sirolimus was not genotoxic in the in vitro bacterial reverse mutation assay, the Chinese hamster ovary cell chromosomal aberration assay, the mouse lymphoma cell forward mutation assay, or the in vivo mouse micronucleus assay.

When female rats were treated by oral gavage with sirolimus and mated to untreated males, female fertility was decreased at 0.5 mg/kg (2.5-fold the clinical dose of 2 mg, on a body surface area basis) due to decreased implantation. In addition, reduced ovary and uterus weight were observed. The NOAEL for female rat fertility was 0.1 mg/kg (0.5-fold the clinical dose of 2 mg).

When male rats were treated by oral gavage with sirolimus and mated to untreated females, male fertility was decreased at 2 mg/kg (9.7-fold the clinical dose of 2 mg, on a body surface area basis). Atrophy of testes, epididymides, prostate, seminiferous tubules, and reduced sperm counts were observed. The NOAEL for male rat fertility was 0.5 mg/kg (2.5-fold the clinical dose of 2 mg).

Testicular tubular degeneration was also seen in a 4-week intravenous study of sirolimus in monkeys at 0.1 mg/kg (1-fold the clinical dose of 2 mg, on a body surface area basis).

14 CLINICAL STUDIES

14.1 Prophylaxis of Organ Rejection in Renal Transplant Patients

Sirolimus Oral Solution

The safety and efficacy of sirolimus oral solution for the prevention of organ rejection following renal transplantation were assessed in two randomized, double-blind, multicenter, controlled trials. These studies compared two dose levels of sirolimus oral solution (2 mg and 5 mg, once daily) with azathioprine (Study 1) or placebo (Study 2) when administered in combination with cyclosporine and corticosteroids. Study 1 was conducted in the United States at 38 sites. Seven hundred nineteen (719) patients were enrolled in this trial and randomized following transplantation; 284 were randomized to receive sirolimus oral solution 2 mg/day; 274 were randomized to receive sirolimus oral solution 5 mg/day, and 161 to receive azathioprine 2–3 mg/kg/day. Study 2 was conducted in Australia, Canada, Europe, and the United States, at a total of 34 sites. Five hundred seventy-six (576) patients were enrolled in this trial and randomized before transplantation; 227 were randomized to receive sirolimus oral solution 2 mg/day; 219 were randomized to receive sirolimus oral solution 5 mg/day, and 130 to receive placebo. In both studies, the use of antilymphocyte antibody induction therapy was prohibited. In both studies, the primary efficacy endpoint was the rate of efficacy failure in the first 6 months after transplantation. Efficacy failure was defined as the first occurrence of an acute rejection episode (confirmed by biopsy), graft loss, or death.

The tables below summarize the results of the primary efficacy analyses from these trials. sirolimus oral solution, at doses of 2 mg/day and 5 mg/day, significantly reduced the incidence of efficacy failure (statistically significant at the <0.025 level; nominal significance level adjusted for multiple [2] dose comparisons) at 6 months following transplantation compared with both azathioprine and placebo.

TABLE 8: INCIDENCE (%) OF EFFICACY FAILURE AT 6 AND 24 MONTHS FOR STUDY 1 [Patients received cyclosporine and corticosteroids.] , [Includes patients who prematurely discontinued treatment.]
Parameter | Sirolimus Oral Solution 2 mg/day (n = 284) | Sirolimus Oral Solution 5 mg/day (n = 274) | Azathioprine 2–3 mg/kg/day (n = 161)
Efficacy failure at 6 months [Primary endpoint.] | 18.7 | 16.8 | 32.3
Components of efficacy failure
Biopsy-proven acute rejection | 16.5 | 11.3 | 29.2
Graft loss | 1.1 | 2.9 | 2.5
Death | 0.7 | 1.8 | 0
Lost to follow-up | 0.4 | 0.7 | 0.6
Efficacy failure at 24 months | 32.8 | 25.9 | 36.0
Components of efficacy failure
Biopsy-proven acute rejection | 23.6 | 17.5 | 32.3
Graft loss | 3.9 | 4.7 | 3.1
Death | 4.2 | 3.3 | 0
Lost to follow-up | 1.1 | 0.4 | 0.6

TABLE 9: INCIDENCE (%) OF EFFICACY FAILURE AT 6 AND 36 MONTHS FOR STUDY 2 [Patients received cyclosporine and corticosteroids.] , [Includes patients who prematurely discontinued treatment.]
Parameter | Sirolimus Oral Solution 2 mg/day (n = 227) | Sirolimus Oral Solution 5 mg/day (n = 219) | Placebo (n = 130)
Efficacy failure at 6 months [Primary endpoint.] | 30.0 | 25.6 | 47.7
Components of efficacy failure
Biopsy-proven acute rejection | 24.7 | 19.2 | 41.5
Graft loss | 3.1 | 3.7 | 3.9
Death | 2.2 | 2.7 | 2.3
Lost to follow-up | 0 | 0 | 0
Efficacy failure at 36 months | 44.1 | 41.6 | 54.6
Components of efficacy failure
Biopsy-proven acute rejection | 32.2 | 27.4 | 43.9
Graft loss | 6.2 | 7.3 | 4.6
Death | 5.7 | 5.9 | 5.4
Lost to follow-up | 0 | 0.9 | 0.8

Patient and graft survival at 1 year were co-primary endpoints. The following table shows graft and patient survival at 1 and 2 years in Study 1, and 1 and 3 years in Study 2. The graft and patient survival rates were similar in patients treated with sirolimus and comparator-treated patients.

TABLE 10: GRAFT AND PATIENT SURVIVAL (%) FOR STUDY 1 (12 AND 24 MONTHS) AND STUDY 2 (12 AND 36 MONTHS) [Patients received cyclosporine and corticosteroids.] , [Includes patients who prematurely discontinued treatment.]
Parameter | Sirolimus Oral Solution 2 mg/day | Sirolimus Oral Solution 5 mg/day | Azathioprine 2–3 mg/kg/day | Placebo
Study 1 | (n = 284) | (n = 274) | (n = 161)
Graft survival
Month 12 | 94.7 | 92.7 | 93.8
Month 24 | 85.2 | 89.1 | 90.1
Patient survival
Month 12 | 97.2 | 96.0 | 98.1
Month 24 | 92.6 | 94.9 | 96.3
Study 2 | (n = 227) | (n = 219) |  | (n = 130)
Graft survival
Month 12 | 89.9 | 90.9 |  | 87.7
Month 36 | 81.1 | 79.9 |  | 80.8
Patient survival
Month 12 | 96.5 | 95.0 |  | 94.6
Month 36 | 90.3 | 89.5 |  | 90.8

The reduction in the incidence of first biopsy-confirmed acute rejection episodes in patients treated with sirolimus compared with the control groups included a reduction in all grades of rejection.

In Study 1, which was prospectively stratified by race within center, efficacy failure was similar for sirolimus oral solution 2 mg/day and lower for sirolimus oral solution 5 mg/day compared with azathioprine in Black patients. In Study 2, which was not prospectively stratified by race, efficacy failure was similar for both sirolimus oral solution doses compared with placebo in Black patients. The decision to use the higher dose of sirolimus oral solution in Black patients must be weighed against the increased risk of dose-dependent adverse events that were observed with the sirolimus oral solution 5-mg dose [see Adverse Reactions (6.1)].

TABLE 11: PERCENTAGE OF EFFICACY FAILURE BY RACE AT 6 MONTHS [Patients received cyclosporine and corticosteroids.] , [Includes patients who prematurely discontinued treatment.]
Parameter | Sirolimus Oral Solution 2 mg/day | Sirolimus Oral Solution 5 mg/day | Azathioprine 2–3 mg/kg/day | Placebo
Study 1
Black (n = 166) | 34.9 (n = 63) | 18.0 (n = 61) | 33.3 (n = 42)
Non-Black (n = 553) | 14.0 (n = 221) | 16.4 (n = 213) | 31.9 (n = 119)
Study 2
Black (n = 66) | 30.8 (n = 26) | 33.7 (n = 27) |  | 38.5 (n = 13)
Non-Black (n = 510) | 29.9 (n = 201) | 24.5 (n = 192) |  | 48.7 (n = 117)

Mean glomerular filtration rates (GFR) post-transplant were calculated by using the Nankivell equation at 12 and 24 months for Study 1, and 12 and 36 months for Study 2. Mean GFR was lower in patients treated with cyclosporine and sirolimus oral solution compared with those treated with cyclosporine and the respective azathioprine or placebo control.

TABLE 12: OVERALL CALCULATED GLOMERULAR FILTRATION RATES (Mean ± SEM, cc/min) BY NANKIVELL EQUATION POST-TRANSPLANT [Includes patients who prematurely discontinued treatment.] , [Patients who had a graft loss were included in the analysis with GFR set to 0.0.]
Parameter | Sirolimus Oral Solution 2 mg/day | Sirolimus Oral Solution 5 mg/day | Azathioprine 2–3 mg/kg/day | Placebo
Study 1
Month 12 | 57.4 ± 1.3 (n = 269) | 54.6 ± 1.3 (n = 248) | 64.1 ± 1.6) (n = 149)
Month 24 | 58.4 ± 1.5 (n = 221) | 52.6 ± 1.5 (n = 222) | 62.4 ± 1.9 (n = 132)
Study 2
Month 12 | 52.4 ± 1.5 (n = 211) | 51.5 ± 1.5 (n = 199) |  | 58.0 ± 2.1 (n = 117)
Month 36 | 48.1 ± 1.8 (n = 183) | 46.1 ± 2.0 (n = 177) |  | 53.4 ± 2.7 (n = 102)

Within each treatment group in Studies 1 and 2, mean GFR at one-year post-transplant was lower in patients who experienced at least one episode of biopsy-proven acute rejection, compared with those who did not.

Renal function should be monitored, and appropriate adjustment of the immunosuppressive regimen should be considered in patients with elevated or increasing serum creatinine levels [see Warnings and Precautions (5.8)].

Sirolimus Tablets

The safety and efficacy of sirolimus oral solution and sirolimus tablets for the prevention of organ rejection following renal transplantation were demonstrated to be clinically equivalent in a randomized, multicenter, controlled trial [see Clinical Pharmacology (12.3)].

14.2 Cyclosporine Withdrawal Study in Renal Transplant Patients

The safety and efficacy of sirolimus as a maintenance regimen were assessed following cyclosporine withdrawal at 3 to 4 months after renal transplantation. Study 3 was a randomized, multicenter, controlled trial conducted at 57 centers in Australia, Canada, and Europe. Five hundred twenty-five (525) patients were enrolled. All patients in this study received the tablet formulation. This study compared patients who were administered sirolimus, cyclosporine, and corticosteroids continuously with patients who received this same standardized therapy for the first 3 months after transplantation (pre-randomization period) followed by the withdrawal of cyclosporine. During cyclosporine withdrawal, the sirolimus dosages were adjusted to achieve targeted sirolimus whole blood trough concentration ranges (16 to 24 ng/mL until month 12, then 12 to 20 ng/mL thereafter, expressed as chromatographic assay values). At 3 months, 430 patients were equally randomized to either continue sirolimus with cyclosporine therapy or to receive sirolimus as a maintenance regimen following cyclosporine withdrawal.

Eligibility for randomization included no Banff Grade 3 acute rejection or vascular rejection episode in the 4 weeks before random assignment, serum creatinine ≤4.5 mg/dL, and adequate renal function to support cyclosporine withdrawal (in the opinion of the investigator). The primary efficacy endpoint was graft survival at 12 months after transplantation. Secondary efficacy endpoints were the rate of biopsy-confirmed acute rejection, patient survival, incidence of efficacy failure (defined as the first occurrence of either biopsy-proven acute rejection, graft loss, or death), and treatment failure (defined as the first occurrence of either discontinuation, acute rejection, graft loss, or death).

The following table summarizes the resulting graft and patient survival at 12, 24, and 36 months for this trial. At 12, 24, and 36 months, graft and patient survival were similar for both groups.

TABLE 13: GRAFT AND PATIENT SURVIVAL (%): STUDY 3 [Includes patients who prematurely discontinued treatment.]
Parameter | Sirolimus with Cyclosporine Therapy (n = 215) | Sirolimus Following Cyclosporine Withdrawal (n = 215)
Graft Survival
Month 12 [Primary efficacy endpoint.] | 95.3 [Survival including loss to follow-up as an event.] | 97.2
Month 24 | 91.6 | 94.0
Month 36 [Initial planned duration of the study.] | 87.0 | 91.6
Patient Survival
Month 12 | 97.2 | 98.1
Month 24 | 94.4 | 95.8
Month 36 | 91.6 | 94.0

The following table summarizes the results of first biopsy-proven acute rejection at 12 and 36 months. There was a significant difference in first biopsy-proven rejection rates between the two groups after randomization and through 12 months. Most of the post-randomization acute rejections occurred in the first 3 months following randomization.

TABLE 14: INCIDENCE OF FIRST BIOPSY-PROVEN ACUTE REJECTION (%) BY TREATMENT GROUP AT 36 MONTHS: STUDY 3 [Includes patients who prematurely discontinued treatment.] , [All patients received corticosteroids.]
Period | Sirolimus with Cyclosporine Therapy (n = 215) | Sirolimus Following Cyclosporine Withdrawal (n = 215)
Pre-randomization [Randomization occurred at 3 months ± 2 weeks.] | 9.3 | 10.2
Post-randomization through 12 months | 4.2 | 9.8
Post-randomization from 12 to 36 months | 1.4 | 0.5
Post-randomization through 36 months | 5.6 | 10.2
Total at 36 months | 14.9 | 20.5

Patients receiving renal allografts with ≥4 HLA mismatches experienced significantly higher rates of acute rejection following randomization to the cyclosporine withdrawal group, compared with patients who continued cyclosporine (15.3% versus 3.0%). Patients receiving renal allografts with ≤3 HLA mismatches demonstrated similar rates of acute rejection between treatment groups (6.8% versus 7.7%) following randomization.

The following table summarizes the mean calculated GFR in Study 3 (cyclosporine withdrawal study).

TABLE 15: CALCULATED GLOMERULAR FILTRATION RATES (mL/min) BY NANKIVELL EQUATION AT 12, 24, AND 36 MONTHS POST-TRANSPLANT: STUDY 3 [Includes patients who prematurely discontinued treatment.] , [Patients who had a graft loss were included in the analysis and had their GFR set to 0.0.] , [All patients received corticosteroids.]
Parameter | Sirolimus with Cyclosporine Therapy | Sirolimus Following Cyclosporine Withdrawal
Month 12
Mean ± SEM | 53.2 ± 1.5 (n = 208) | 59.3 ± 1.5 (n = 203)
Month 24
Mean ± SEM | 48.4 ± 1.7 (n = 203) | 58.4 ± 1.6 (n = 201)
Month 36
Mean ± SEM | 47.0 ± 1.8 (n = 196) | 58.5 ± 1.9 (n = 199)

The mean GFR at 12, 24, and 36 months, calculated by the Nankivell equation, was significantly higher for patients receiving sirolimus as a maintenance regimen following cyclosporine withdrawal than for those in the sirolimus with cyclosporine therapy group. Patients who had an acute rejection prior to randomization had a significantly higher GFR following cyclosporine withdrawal compared to those in the sirolimus with cyclosporine group. There was no significant difference in GFR between groups for patients who experienced acute rejection post-randomization.

Although the initial protocol was designed for 36 months, there was a subsequent amendment to extend this study. The results for the cyclosporine withdrawal group at months 48 and 60 were consistent with the results at month 36. Fifty-two percent (112/215) of the patients in the sirolimus with cyclosporine withdrawal group remained on therapy to month 60 and showed sustained GFR.

14.3 High-Immunologic Risk Renal Transplant Patients

Sirolimus was studied in a one-year, clinical trial in high risk patients (Study 4) who were defined as Black transplant recipients and/or repeat renal transplant recipients who lost a previous allograft for immunologic reasons and/or patients with high panel-reactive antibodies (PRA; peak PRA level >80%). Patients received concentration-controlled sirolimus and cyclosporine (MODIFIED), and corticosteroids per local practice. The sirolimus dose was adjusted to achieve target whole blood trough sirolimus concentrations of 10–15 ng/mL (chromatographic method) throughout the 12-month study period. The cyclosporine dose was adjusted to achieve target whole blood trough concentrations of 200–300 ng/mL through week 2, 150–200 ng/mL from week 2 to week 26, and 100–150 ng/mL from week 26 to week 52 [see Clinical Pharmacology (12.3)] for the observed trough concentrations ranges. Antibody induction was allowed per protocol as prospectively defined at each transplant center, and was used in 88.4% of patients. The study was conducted at 35 centers in the United States. A total of 224 patients received a transplant and at least one dose of sirolimus and cyclosporine and was comprised of 77.2% Black patients, 24.1% repeat renal transplant recipients, and 13.5% patients with high PRA. Efficacy was assessed with the following endpoints, measured at 12 months: efficacy failure (defined as the first occurrence of biopsy-confirmed acute rejection, graft loss, or death), first occurrence of graft loss or death, and renal function as measured by the calculated GFR using the Nankivell formula. The table below summarizes the result of these endpoints.

TABLE 16: EFFICACY FAILURE, GRAFT LOSS OR DEATH AND CALCULATED GLOMERULAR FUNCTION RATES (mL/min) BY NANKIVELL EQUATION AT 12 MONTHS POST-TRANSPLANT: STUDY 4
Parameter | Sirolimus with Cyclosporine, Corticosteroids (n = 224)
Efficacy Failure (%) | 23.2
Graft Loss or Death (%) | 9.8
Renal Function (mean ± SEM) [Calculated glomerular filtration rate by Nankivell equation.] , [Patients who had graft loss were included in this analysis with GFR set to 0.] | 52.6 ± 1.6 (n = 222)

Patient survival at 12 months was 94.6%. The incidence of biopsy-confirmed acute rejection was 17.4% and the majority of the episodes of acute rejection were mild in severity.

14.4 Conversion from Calcineurin Inhibitors to Sirolimus in Maintenance Renal Transplant Patients

Conversion from calcineurin inhibitors (CNI) to sirolimus was assessed in maintenance renal transplant patients 6 months to 10 years post-transplant (Study 5). This study was a randomized, multicenter, controlled trial conducted at 111 centers globally, including US and Europe, and was intended to show that renal function was improved by conversion from CNI to sirolimus. Eight hundred thirty (830) patients were enrolled and stratified by baseline calculated glomerular filtration rate (GFR, 20–40 mL/min versus greater than 40 mL/min). In this trial there was no benefit associated with conversion with regard to improvement in renal function and a greater incidence of proteinuria in the sirolimus conversion arm. In addition, enrollment of patients with baseline calculated GFR less than 40 mL/min was discontinued due to a higher rate of serious adverse events, including pneumonia, acute rejection, graft loss and death [see Adverse Reactions (6.4)].

This study compared renal transplant patients (6–120 months after transplantation) who were converted from calcineurin inhibitors to sirolimus, with patients who continued to receive calcineurin inhibitors. Concomitant immunosuppressive medications included mycophenolate mofetil (MMF), azathioprine (AZA), and corticosteroids. Sirolimus was initiated with a single loading dose of 12–20 mg, after which dosing was adjusted to achieve a target sirolimus whole blood trough concentration of 8–20 ng/mL (chromatographic method). The efficacy endpoint was calculated GFR at 12 months post-randomization. Additional endpoints included biopsy-confirmed acute rejection, graft loss, and death. Findings in the patient stratum with baseline calculated GFR greater than 40 mL/min (sirolimus conversion, n = 497; CNI continuation, n = 246) are summarized below. There was no clinically or statistically significant improvement in Nankivell GFR compared to baseline.

TABLE 17: RENAL FUNCTION IN STABLE RENAL TRANSPLANT PATIENTS IN PATIENTS WITH BASELINE GFR >40 mL/min THE SIROLIMUS CONVERSION STUDY (STUDY 5)
Parameter | Sirolimus Conversion N=496 | CNI Continuation N=245 | Difference (95% CI)
GFR mL/min (Nankivell) at 1 year | 59.0 | 57.7 | 1.3 (-1.1, 3.7)
GFR mL/min (Nankivell) at 2 year | 53.7 | 52.1 | 1.6 (-1.4, 4.6)

The rates of acute rejection, graft loss, and death were similar at 1 and 2 years. Treatment-emergent adverse events occurred more frequently during the first 6 months after sirolimus conversion. The rates of pneumonia were significantly higher for the sirolimus conversion group.

While the mean and median values for urinary protein to creatinine ratio were similar between treatment groups at baseline, significantly higher mean and median levels of urinary protein excretion were seen in the sirolimus conversion arm at 1 year and at 2 years, as shown in the table below [see Warnings and Precautions (5.9)]. In addition, when compared to patients who continued to receive calcineurin inhibitors, a higher percentage of patients had urinary protein to creatinine ratios >1 at 1 and 2 years after sirolimus conversion. This difference was seen in both patients who had a urinary protein to creatinine ratio ≤1 and those who had a protein to creatinine ratio >1 at baseline. More patients in the sirolimus conversion group developed nephrotic range proteinuria, as defined by a urinary protein to creatinine ratio >3.5 (46/482 [9.5%] versus 9/239 [3.8%]), even when the patients with baseline nephrotic range proteinuria were excluded. The rate of nephrotic range proteinuria was significantly higher in the sirolimus conversion group compared to the calcineurin inhibitor continuation group with baseline urinary protein to creatinine ratio >1 (13/29 versus 1/14), excluding patients with baseline nephrotic range proteinuria.

TABLE 18: MEAN AND MEDIAN VALUES FOR URINARY PROTEIN TO CREATININE RATIO (mg/mg) BETWEEN TREATMENT GROUPS AT BASELINE, 1 AND 2 YEARS IN THE STRATUM WITH BASELINE CALCULATED GFR >40 mL/min
Study period | Sirolimus Conversion |  |  | CNI Continuation
 | N | Mean ± SD | Median | N | Mean ± SD | Median | p-value
Baseline | 410 | 0.35 ± 0.76 | 0.13 | 207 | 0.28 ± 0.61 | 0.11 | 0.381
1 year | 423 | 0.88 ± 1.61 | 0.31 | 203 | 0.37 ± 0.88 | 0.14 | <0.001
2 years | 373 | 0.86 ± 1.48 | 0.32 | 190 | 0.47 ± 0.98 | 0.13 | <0.001

The above information should be taken into account when considering conversion from calcineurin inhibitors to sirolimus in stable renal transplant patients due to the lack of evidence showing that renal function improves following conversion, and the finding of a greater increment in urinary protein excretion, and an increased incidence of treatment-emergent nephrotic range proteinuria following conversion to sirolimus. This was particularly true among patients with existing abnormal urinary protein excretion prior to conversion.

In an open-label, randomized, comparative, multicenter study where kidney transplant patients were either converted from tacrolimus to sirolimus 3 to 5 months post-transplant (sirolimus group) or remained on tacrolimus, there was no significant difference in renal function at 2 years post-transplant. Overall, 44/131 (33.6%) discontinued treatment in the sirolimus group versus 12/123 (9.8%) in the tacrolimus group. More patients reported adverse events 130/131 (99.2%) versus 112/123 (91.1%) and more patients reported discontinuations from the treatment due to adverse events 28/131 (21.4%) versus 4/123 (3.3%) in the sirolimus group compared to the tacrolimus group.

The incidence of biopsy-confirmed acute rejection was higher for patients in the sirolimus group 11/131 (8.4%) compared to the tacrolimus group 2/123 (1.6%) through 2 years post-transplant. The rate of new-onset diabetes mellitus post-randomization, defined as 30 days or longer of continuous or at least 25 days non-stop (without gap) use of any diabetic treatment after randomization, a fasting glucose ≥126 mg/dL or a non-fasting glucose ≥200 mg/dL, was higher in the sirolimus group 15/82 (18.3%) compared to the tacrolimus group 4/72 (5.6%). A greater incidence of proteinuria, was seen in the sirolimus group 19/131 (14.5%) versus 2/123 (1.6%) in the tacrolimus group.

14.5 Conversion from a CNI-based Regimen to a Sirolimus-based Regimen in Liver Transplant Patients

Conversion from a CNI-based regimen to a sirolimus-based regimen was assessed in stable liver transplant patients 6–144 months post-transplant. The clinical study was a 2:1 randomized, multi-center, controlled trial conducted at 82 centers globally, including the US and Europe, and was intended to show that renal function was improved by conversion from a CNI to sirolimus without adversely impacting efficacy or safety. A total of 607 patients were enrolled.

The study failed to demonstrate superiority of conversion to a sirolimus-based regimen compared to continuation of a CNI-based regimen in baseline-adjusted GFR, as estimated by Cockcroft-Gault, at 12 months (62 mL/min in the sirolimus conversion group and 63 mL/min in the CNI continuation group). The study also failed to demonstrate non-inferiority, with respect to the composite endpoint consisting of graft loss and death (including patients with missing survival data) in the sirolimus conversion group compared to the CNI continuation group (6.6% versus 5.6%). The number of deaths in the sirolimus conversion group (15/393, 3.8%) was higher than in the CNI continuation group (3/214, 1.4%), although the difference was not statistically significant. The rates of premature study discontinuation (primarily due to adverse events or lack of efficacy), adverse events overall (infections, specifically), and biopsy-proven acute liver graft rejection at 12 months were all significantly greater in the sirolimus conversion group compared to the CNI continuation group.

14.6 Pediatric Renal Transplant Patients

Sirolimus was evaluated in a 36-month, open-label, randomized, controlled clinical trial at 14 North American centers in pediatric (aged 3 to <18 years) renal transplant patients considered to be at high-immunologic risk for developing chronic allograft nephropathy, defined as a history of one or more acute allograft rejection episodes and/or the presence of chronic allograft nephropathy on a renal biopsy. Seventy-eight (78) subjects were randomized in a 2:1 ratio to sirolimus (sirolimus target concentrations of 5 to 15 ng/mL, by chromatographic assay, n = 53) in combination with a calcineurin inhibitor and corticosteroids or to continue calcineurin-inhibitor-based immunosuppressive therapy (n = 25). The primary endpoint of the study was efficacy failure as defined by the first occurrence of biopsy-confirmed acute rejection, graft loss, or death, and the trial was designed to show superiority of sirolimus added to a calcineurin-inhibitor-based immunosuppressive regimen compared to a calcineurin-inhibitor-based regimen. The cumulative incidence of efficacy failure up to 36 months was 45.3% in the sirolimus group compared to 44.0% in the control group, and did not demonstrate superiority. There was one death in each group. The use of sirolimus in combination with calcineurin inhibitors and corticosteroids was associated with an increased risk of deterioration of renal function, serum lipid abnormalities (including, but not limited to, increased serum triglycerides and cholesterol), and urinary tract infections [see Warnings and Precautions (5.8)]. This study does not support the addition of sirolimus to calcineurin-inhibitor-based immunosuppressive therapy in this subpopulation of pediatric renal transplant patients.

14.7 Lymphangioleiomyomatosis Patients

The safety and efficacy of sirolimus for treatment of lymphangioleiomyomatosis (LAM) were assessed in a randomized, double-blind, multicenter, controlled trial. This study compared sirolimus (dose-adjusted to maintain blood trough concentrations between 5–15 ng/mL) with placebo for a 12-month treatment period, followed by a 12-month observation period. Eighty-nine (89) patients were enrolled; 43 patients were randomized to receive placebo and 46 patients to receive sirolimus. The primary endpoint was the difference between the groups in the rate of change (slope) per month in forced expiratory volume in 1 second (FEV1). During the treatment period, the FEV1 slope was -12±2 mL per month in the placebo group and 1±2 mL per month in the sirolimus group (treatment difference = 13 mL (95% CI: 7, 18). The absolute between-group difference in the mean change in FEV1 during the 12-month treatment period was 153 mL, or approximately 11% of the mean FEV1 at enrollment. Similar improvements were seen for forced vital capacity (FVC). After discontinuation of sirolimus, the decline in lung function resumed in the sirolimus group and paralleled that in the placebo group (see Figure 1).

FIGURE 1: CHANGE IN FORCED EXPIRATORY VOLUME IN 1 SECOND (FEV1) DURING THE TREATMENT AND OBSERVATION PHASES OF THE STUDY IN LAM PATIENTS

The rate of change over 12 months of vascular endothelial growth factor-D (VEGF-D), a lymphangiogenic growth factor which has been shown to be elevated in patients with LAM, was significantly different in the sirolimus-treated group (-88.0 ± 16.6 pg/mL/month) compared to placebo (-2.42 ± 17.2 pg/mL/month) with a treatment difference of -86 pg/mL/month (95% CI: -133, -39). The absolute between-group difference in the mean change in VEGF-D during the 12-month treatment period was -1017.2, or approximately 50% of the mean VEGF-D at enrollment.

15 REFERENCES

Clinical Therapeutics, Volume 22, Supplement B, April 2000 [see Dosage and Administration (2.5)].

16 HOW SUPPLIED/STORAGE AND HANDLING

Since sirolimus is not absorbed through the skin, there are no special precautions. However, if direct contact of the oral solution occurs with the skin or eyes, wash skin thoroughly with soap and water; rinse eyes with plain water.

Do not use sirolimus after the expiration date. The expiration date refers to the last day of that month.

16.1 Sirolimus Oral Solution

Each sirolimus oral solution carton, NDC 59762-1205-6, contains one 2 oz (60 mL fill) amber glass bottle of sirolimus (concentration of 1 mg/mL), one oral syringe adapter for fitting into the neck of the bottle, sufficient disposable oral syringes (amber color) and caps for daily dosing, and a carrying case.

STORAGE AND HANDLING

Sirolimus oral solution bottles should be stored protected from light and refrigerated at 2°C to 8°C (36°F to 46°F). Once the bottle is opened, the contents should be used within one month. If necessary, the patient may store the bottles at room temperatures up to 25°C (77°F) for a short period of time (e.g., not more than 15 days for the bottles).

A syringe (amber color) and cap are provided for dosing, and the product may be kept in the syringe for a maximum of 24 hours at room temperatures up to 25°C (77°F) or refrigerated at 2°C to 8°C (36°F to 46°F). The syringe should be discarded after one use. After dilution, the preparation should be used immediately.

Sirolimus oral solution provided in bottles may develop a slight haze when refrigerated. If such a haze occurs, allow the product to stand at room temperature and shake gently until the haze disappears. The presence of this haze does not affect the quality of the product.

17 PATIENT COUNSELING INFORMATION

Advise patients, their families, and their caregivers to read the Medication Guide and Instructions for Use and assist them in understanding its contents. The complete text of the Medication Guide and Instructions for Use are reprinted at the end of the document.

See FDA-Approved Medication Guide and Instructions for Use.

17.1 Dosage

Patients should be given complete dosage instructions [see FDA-Approved Medication Guide].

17.2 Skin Cancer Events

Advise patients that exposure to sunlight and ultraviolet (UV) light should be limited by wearing protective clothing and using a broad spectrum sunscreen with a high protection factor because of the increased risk for skin cancer [see Warnings and Precautions (5.18)].

17.3 Pregnancy and Lactation

Advise female patients of reproductive potential to avoid becoming pregnant throughout treatment and for 12 weeks after sirolimus therapy has stopped. Sirolimus can cause fetal harm if taken during pregnancy. Advise a pregnant woman of the potential risk to her fetus. Before making a decision to breastfeed, inform the patient that the effects of breastfeeding in infants while taking this drug are unknown, but there is potential for serious adverse effects [see Warnings and Precautions (5.15), Use in Specific Populations (8.1, 8.2, 8.3)].

17.4 Infertility

Inform male and female patients that sirolimus may impair fertility [see Warnings and Precautions (5.16), Adverse Reactions (6.7), Use in Specific Populations (8.1, 8.3), Nonclinical Toxicology (13.1)].

LAB-0686-13.0

MEDICATION GUIDE
Sirolimus Oral Solution

What is the most important information I should know about sirolimus?
Sirolimus can cause serious side effects, including:

- Increased risk of getting infections. Serious infections can happen including infections caused by viruses, bacteria, and fungi (yeast). Your doctor may put you on medicine to help prevent some of these infections.
  Call your doctor right away if you have symptoms of infection including fever or chills while taking sirolimus.
- Increased risk of getting certain cancers. People who take sirolimus have a higher risk of getting lymphoma, and other cancers, especially skin cancer. Talk with your doctor about your risk for cancer.

Sirolimus has not been shown to be safe and effective in people who have had liver or lung transplants. Serious complications and death may happen in people who take sirolimus after a liver or lung transplant. You should not take sirolimus if you have had a liver or lung transplant without talking with your doctor.
See the section "What are the possible side effects of sirolimus?" for information about other side effects of sirolimus.

What is sirolimus?
Sirolimus is a prescription medicine used to prevent rejection (anti-rejection medicine) in people 13 years of age and older who have received a kidney transplant. Rejection is when your body's immune system recognizes the new organ as a "foreign" threat and attacks it.
Sirolimus is used with other medicines called cyclosporine (Gengraf, Neoral, Sandimmune), and corticosteroids. Your doctor will decide:

- if sirolimus is right for you, and
- how to best use it with cyclosporine and corticosteroids after your transplant.

It is not known if sirolimus is safe and effective in children under 13 years of age.
Sirolimus is a prescription medicine also used to treat lymphangioleiomyomatosis (LAM). LAM is a rare progressive lung disease that affects predominantly women of childbearing age.

Who should not take sirolimus?
Do not take sirolimus if you are allergic to sirolimus or any of the other ingredients in sirolimus. See the end of this leaflet for a complete list of ingredients in sirolimus.

What should I tell my doctor before taking sirolimus?

- have liver problems
- have skin cancer or it runs in your family
- have high cholesterol or triglycerides (fat in your blood)
- are pregnant or are a female who can become pregnant. Sirolimus can harm your unborn baby. You should not become pregnant during treatment with sirolimus and for 12 weeks after ending treatment with sirolimus. In order to avoid pregnancy, a female who can get pregnant should use effective birth control during treatment and for 12 weeks after your final dose of sirolimus. Talk with your doctor about what birth control method is right for you during this time. Tell your doctor right away if you become pregnant or think you are pregnant during treatment with sirolimus or within 12 weeks after your final dose of sirolimus.
- It is not known whether sirolimus passes into breast milk; however, there is a risk of serious side effects in breastfed infants. You and your doctor should decide about the best way to feed your baby if you take sirolimus.

Tell your doctor about all the medicines you take, including prescription and over-the-counter medicines, vitamins and herbal supplements. Using sirolimus with certain medicines may affect each other causing serious side effects.
Sirolimus may affect the way other medicines work, and other medicines may affect how sirolimus works.
Especially tell your doctor if you take:

- a medicine to lower your cholesterol or triglycerides
- cyclosporine (including Gengraf, Neoral, Sandimmune) or tacrolimus (Prograf) or other medicines that suppress the immune system
- an antibiotic
- an antifungal medicine
- a medicine for high blood pressure or heart problems
- an anti-seizure medicine
- medicines used to treat stomach acid, ulcers, or other gastrointestinal problems
- bromocriptine mesylate (Parlodel, Cycloset)
- danazol
- letermovir (Prevymis)
- medicines to treat HIV or hepatitis C
- St.John’s Wort
- Cannabidiol (Epidiolex)

How should I take sirolimus?

- Read the Instructions for Use that comes with your sirolimus for information about the right way to take sirolimus oral solution.
- Take sirolimus exactly as your doctor tells you to take it.
- Your doctor will tell you how much sirolimus to take and when to take it. Do not change your dose of sirolimus unless your doctor tells you to.
- If you also take cyclosporine (Gengraf, Neoral, Sandimmune), you should take your sirolimus and cyclosporine about 4 hours apart.
- Do not stop taking sirolimus or your other anti-rejection medicines unless your doctor tells you to.
- Your doctor will check the levels of sirolimus in your blood. Your doctor may change your dose of sirolimus depending on your blood test results.
- Sirolimus is taken by mouth 1 time each day.
- Take each dose of sirolimus the same way, either with or without food. Food can affect the amount of medicine that gets into your bloodstream. Taking each dose of sirolimus the same way helps keep your blood levels of sirolimus more stable. Do not take sirolimus with grapefruit juice.
- Sirolimus oral solution can develop a slight haze when it is refrigerated. If this happens, bring the sirolimus oral solution to room temperature and then gently shake the bottle until the haze goes away.
- If you get sirolimus oral solution on your skin, wash the area with soap and water.
- If you get sirolimus oral solution in your eyes, rinse your eyes with water.
- If you have taken more medicine than you were told, contact a doctor or go to the nearest hospital emergency department right away.

What should I avoid while taking sirolimus?

- Avoid receiving live vaccines while taking sirolimus. Some vaccines may not work as well while you are taking sirolimus.
- Limit your time in sunlight and UV light. Cover your skin with clothing and use a broad spectrum sunscreen with a high protection factor because of the increased risk for skin cancer with sirolimus.

What are the possible side effects of sirolimus?
Sirolimus may cause serious side effects, including:

- See "What is the most important information I should know about sirolimus?"
- Serious allergic reactions. Tell your doctor or get medical help right away if you get any of following symptoms of an allergic reaction:

- swelling of your face, eyes, or mouth
- trouble breathing or wheezing
- throat tightness

- chest pain or tightness
- feeling dizzy or faint
- rash or peeling of your skin

- Swelling (edema). Fluid may collect in your hands and feet and in various tissues of your body, including in the sac around your heart or lungs. Call your doctor if you have trouble breathing.
- Poor wound healing. Sirolimus may cause your wounds to heal slowly or not heal well. Tell your doctor if you have any redness or drainage, your wound does not heal, or the wound opens up.
- Increased levels of cholesterol and triglycerides (lipids or fat) in your blood. Your doctor should do blood tests to check your lipids during treatment with sirolimus. Your doctor may prescribe treatment with diet, exercise, or medicine if your lipid levels are too high. During treatment with sirolimus, your blood levels of cholesterol and triglycerides may remain high even if you follow your prescribed treatment plan.
- Effects on kidney function. When sirolimus is taken with cyclosporine (Gengraf, Neoral, Sandimmune), the function of your transplanted kidney may be affected. Your doctor should regularly do tests to check your kidney function while you are taking sirolimus with cyclosporine (Gengraf, Neoral, Sandimmune).
- Increased protein in your urine. Your doctor may regularly test your urine protein.
- Increased risk for viral infections.
  - Certain viruses can live in your body and cause active infections when your immune system is weak. BK virus can affect how your kidney works and cause your transplanted kidney to fail.
  - A certain virus can cause a rare serious brain infection called Progressive Multifocal Leukoencephalopathy (PML). PML usually causes death or severe disability. Call your doctor right away if you notice any new or worsening medical problems such as:
    - confusion
    - sudden change in thinking, walking, strength on one side of your body
    - other problems that have lasted over several days
- Lung or breathing problems. This can sometimes lead to death. Tell your doctor if you have a new or worsening cough, shortness of breath, difficulty breathing or any new breathing problems. Your doctor may need to stop sirolimus or lower your dose.
- Blood clotting problems. When sirolimus is taken with cyclosporine or tacrolimus, you may develop a blood clotting problem. Tell your doctor if you get any unexplained bleeding or bruising.
- Possible harm to your unborn baby. Sirolimus can harm your unborn baby. You should not become pregnant during treatment with sirolimus and for 12 weeks after ending treatment with sirolimus. See "What should I tell my doctor before taking sirolimus?".

The most common side effects of sirolimus in people with renal transplant include:

- high blood pressure
- pain (including stomach and joint pain)
- diarrhea
- headache
- fever

- urinary tract infection
- low red blood cell count (anemia)
- nausea
- low platelet count (cells that help blood to clot)
- high blood sugar (diabetes)

The most common side effects of sirolimus in people with LAM include:

- mouth sores
- diarrhea
- stomach pain
- nausea
- sore throat
- acne

- chest pain
- upper respiratory tract infection
- headache
- dizziness
- sore muscles

Other side effects that may occur with sirolimus:

- Sirolimus may affect fertility in females and may affect your ability to become pregnant. Talk to your healthcare provider if this is a concern for you.
- Sirolimus may affect fertility in males and may affect your ability to father a child. Talk to your healthcare provider if this is a concern for you.

Tell your doctor if you have any side effect that bothers you or that does not go away.
These are not all of the possible side effects of sirolimus. For more information ask your doctor or pharmacist.
Call your doctor for medical advice about side effects. You may report side effects to FDA at 1-800-FDA-1088.

How should I store sirolimus?
Sirolimus oral solution:

- Store bottles of sirolimus oral solution in the refrigerator between 36°F to 46°F (2°C to 8°C). Protect from light.
- If necessary, bottles of sirolimus oral solution can be stored at room temperature up to 77°F (25°C) for up to 15 days.
- When a bottle of sirolimus oral solution is opened, it should be used within 1 month.
- Use any diluted sirolimus oral solution right away.

Do not use sirolimus after the expiration date. The expiration date refers to the last day of that month.
Safely throw away medicine that is out of date or no longer needed.
Keep sirolimus and all medicines out of the reach of children.

General information about the safe and effective use of sirolimus.
Medicines are sometimes prescribed for purposes other than those listed in a Medication Guide. Do not use sirolimus for a condition for which it was not prescribed. Do not give sirolimus to other people even if they have the same symptoms that you have. It may harm them.
This Medication Guide summarizes the most important information about sirolimus. If you would like more information talk to your doctor. You can ask your pharmacist or doctor for information about sirolimus that is written for health professionals.
For more information about sirolimus call 1-877-446-3679.

What are the ingredients in sirolimus?
Active ingredients: sirolimus
Inactive ingredients: Inactive ingredients: sirolimus oral solution: Phosal 50 PG® (phosphatidylcholine, propylene glycol, mono- and di-glycerides, ethanol, soy fatty acids, and ascorbyl palmitate) and polysorbate 80. Sirolimus oral solution contains 1.5%–2.5% ethanol.

For sirolimus oral solution:
LAB-0688-8.0

This Medication Guide has been approved by the U.S. Food and Drug Administration. Revised: Nov 2024

INSTRUCTIONS FOR USE

Sirolimus
Oral Solution

Be sure that you read and understand the following instructions for the correct way to dilute and take sirolimus oral solution. Ask your pharmacist or doctor if you are not sure.

Important:

- Always keep the bottle in an upright position.
- You may store sirolimus oral solution that is in a syringe at room temperature up to 77°F (25°C) or in the refrigerator at 36°F to 46°F (2°C to 8°C) for up to 24 hours. See "How should I store sirolimus?" at the end of this Instructions for Use.
- Sirolimus oral solution can develop a slight haze when it is refrigerated. If this happens, bring the sirolimus oral solution to room temperature and then gently shake the bottle until the haze goes away.
- Only use a glass or plastic cup to dilute sirolimus oral solution.
- If you are a caregiver, do not let sirolimus oral solution come in contact with your skin or eyes. If you get the oral solution on your skin, wash the area well with soap and water. If you get the oral solution in your eyes, rinse with plain water.
- If you spill sirolimus oral solution, dry the area with a dry paper towel and then wipe the area with a wet paper towel. Throw away the paper towels in the trash and wash your hands well with soap and water.

Each sirolimus oral solution carton contains:

- a 2 oz. (60 mL fill) amber glass bottle of sirolimus (concentration of 1 mg/mL)
- 1 oral syringe adapter for fitting into the neck of the bottle
- enough disposable oral syringes (amber color) and caps for daily dosing
- 1 carrying case

You will also need:

- glass or plastic cup
- 6 oz. of water or orange juice only

Figure 1: Opening the bottle

1. Open the solution bottle.

- Remove the safety cap by squeezing the tabs on each side of the cap and twisting counterclockwise (Figure 1).

Figure 2: Inserting adapter

2. The first time you use a bottle of sirolimus oral solution:

- Insert the oral syringe adapter (plastic tube with stopper) tightly into the bottle until it is even with the top of the bottle (Figure 2).
- Do not remove the oral syringe adapter from the bottle once inserted.

Figure 3: Inserting syringe

3. Use a new disposable amber oral syringe for each dose of sirolimus oral solution.

- Fully push down (depress) on the plunger of the disposable amber oral syringe.
- Then, tightly insert the oral syringe into the opening in the adapter (Figure 3).

Figure 4: Withdrawing solution

4. Withdraw the prescribed amount of sirolimus oral solution:

- Gently pull back the plunger of the syringe until the level of the oral solution is even with the marking on the syringe for your prescribed dose.
- Always keep the bottle in an upright position.
- If bubbles form within the oral solution in the syringe, empty the syringe into the bottle and repeat step 4 (Figure 4).
- You may need to repeat step 4 more than once to draw up your prescribed dose.

Figure 5: Capping syringe
Figure 6: Placing syringe in carrying case

5. If your doctor tells you to carry your medicine with you:

- Each dose of sirolimus oral solution should be placed in an oral syringe. Place a cap securely on each syringe. The cap should snap into place (Figure 5).
- Place the capped syringe in the enclosed carrying case (Figure 6). If you need more than 1 carrying case, talk with your doctor or pharmacist.
- See 'How should I store sirolimus' for storage instructions.

Figure 7: Emptying syringe into glass

6. Taking a dose of sirolimus oral solution:

- Choose a clean flat work surface. Place a clean paper towel on the work surface. Wash and dry your hands.
- Empty the syringe into a glass or plastic cup containing at least 2 ounces (1/4 cup, 60 mL) of water or orange juice, stir vigorously for 1 minute and drink right away (Figure 7).
- If more than 1 syringe is needed for your prescribed dose, empty the oral solution from each syringe into the same glass or plastic cup of water or orange juice.
- Refill the container with at least 4 ounces (1/2 cup, 120 mL) of water or orange juice, stir vigorously again and drink the rinse solution. Do not mix sirolimus oral solution with apple juice, grapefruit juice, or other liquids. Only glass or plastic cups should be used to mix sirolimus oral solution.
- The syringe and cap should be used only one time and then thrown away.
- Throw away the paper towel and clean the work surface. Wash your hands.

7. Always store the bottles of medication in the refrigerator.

How should I store sirolimus?

- Store bottles of sirolimus oral solution in the refrigerator at 36°F to 46°F (2°C to 8°C).
- Protect from light.
- Store sirolimus oral solution that is in a syringe at room temperature up to 77°F (25°C) or in the refrigerator at 36°F to 46°F (2°C to 8°C) for up to 24 hours.
- If necessary, bottles of sirolimus oral solution can be stored at room temperature up to 77°F (25°C) for up to 15 days.
- When a bottle of sirolimus oral solution is opened, it should be used within 1 month.
- Use any diluted sirolimus oral solution right away.

Keep sirolimus and all medicines out of the reach of children.

This Instructions for Use has been approved by the U.S. Food and Drug Administration.

LAB-0687-6.0

Revised November 2024

PRINCIPAL DISPLAY PANEL - 60 mL Bottle Label

ALWAYS DISPENSE WITH MEDICATION GUIDE

NDC 59762-1205-4
60 mL bottle

GREENSTONE® BRAND
sirolimus
oral solution

1 mg/mL

For oral use only.
Each mL of sirolimus oral solution contains
1 mg sirolimus.
1.5%-2.5% ethanol
Also contains a mixture of propylene glycol
and phosphatidylcholine derived from soy
lecithin (and other components) and
polysorbate 80.

Rx only

PRINCIPAL DISPLAY PANEL - 60 mL Bottle Carton

ALWAYS DISPENSE WITH
MEDICATION GUIDE

NDC 59762-1205-4
60 mL bottle

GREENSTONE® BRAND

sirolimus
oral solution

1 mg/mL

For oral use only.

Each mL of sirolimus oral
solution contains 1 mg
sirolimus.

1.5%-2.5% ethanol

Also contains a mixture of
propylene glycol and
phosphatidylcholine derived from
soy lecithin (and other
components) and polysorbate 80.

Rx only

PRINCIPAL DISPLAY PANEL - Kit Carton

ALWAYS DISPENSE WITH MEDICATION GUIDE

NDC 59762-1205-6
60 mL patient kit

GREENSTONE® BRAND

sirolimus
oral solution

1 mg/mL

For oral use only.

Each mL of sirolimus oral solution contains 1 mg sirolimus.

1.5%-2.5% ethanol

Also contains a mixture of propylene glycol and phosphatidylcholine
derived from soy lecithin (and other components) and polysorbate 80.

Rx only

Each sirolimus oral solution carton contains:

- A 2 oz. (60 mL fill) amber glass bottle of
  sirolimus (concentration of 1 mg/mL)
- 1 oral syringe adapter for fitting into the neck of
  the bottle
- 30 amber oral syringes and 30 caps for daily
  dosing
- 1 carrying case

Also contains: Package Insert and Medication Guide

You will also need:

- glass or plastic cup
- 6 oz. of water or orange juice only